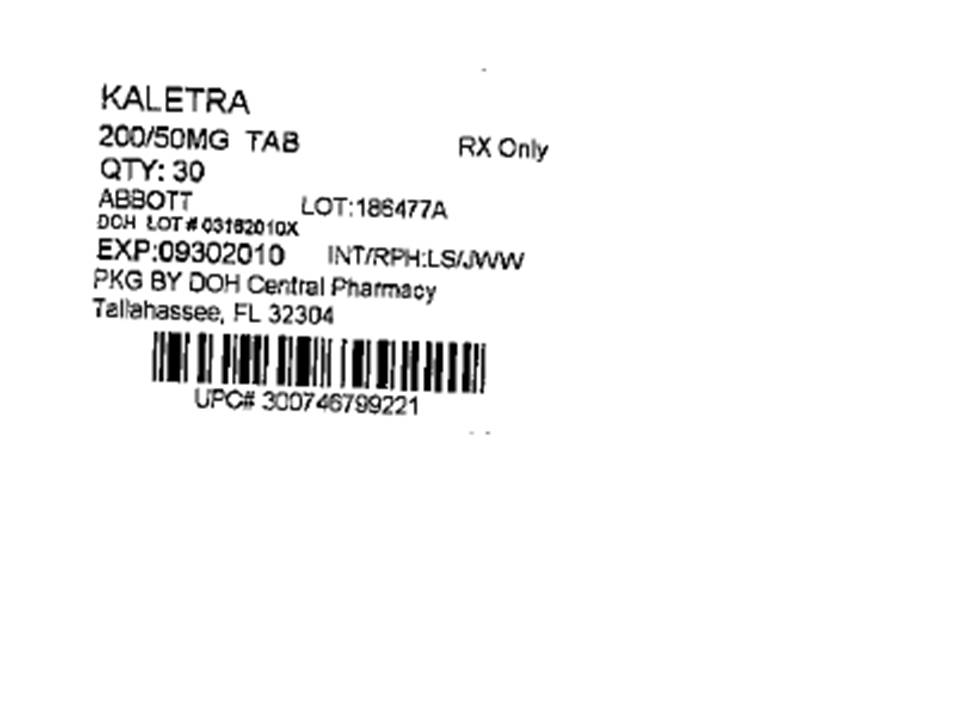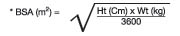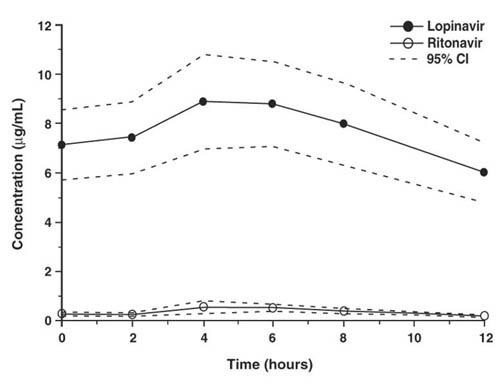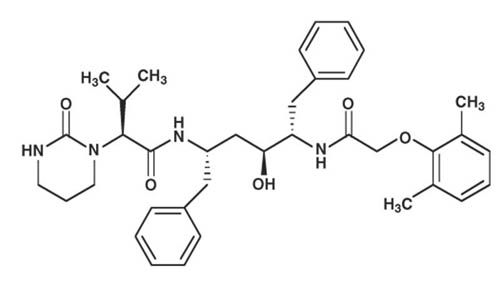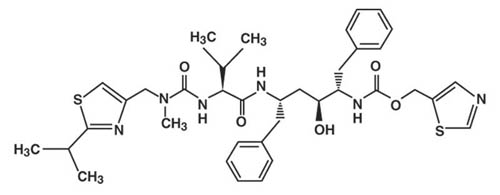 DRUG LABEL: Kaletra
NDC: 53808-0276 | Form: TABLET, FILM COATED
Manufacturer: DOH CENTRAL PHARMACY
Category: prescription | Type: HUMAN PRESCRIPTION DRUG LABEL
Date: 20170203

ACTIVE INGREDIENTS: LOPINAVIR 200 mg/1 1; RITONAVIR 50 mg/1 1
INACTIVE INGREDIENTS: COPOVIDONE K25-31; SORBITAN MONOLAURATE; SILICON DIOXIDE; SODIUM STEARYL FUMARATE; HYPROMELLOSES; TITANIUM DIOXIDE; POLYETHYLENE GLYCOL 400; HYDROXYPROPYL CELLULOSE (TYPE H); TALC; POLYETHYLENE GLYCOL 3350; FERRIC OXIDE YELLOW; POLYSORBATE 80

HIGHLIGHTS OF PRESCRIBING INFORMATION

These highlights do not include all the information needed to use KALETRA safely and effectively. See full prescribing information for KALETRA.
KALETRA (lopinavir/ritonavir) tablets, film coated for oral use
KALETRA (lopinavir/ritonavir) solution for oral use
Initial U.S. Approval: 2000

RECENT MAJOR CHANGES

Contraindications, Table 3 (4) 6/2008
Dosage and Administration, Pediatric Patients (2.2) 6/2008
Warnings and Precautions, PR Interval Prolongation (5.5) 4/2009
Warnings and Precautions, QT Interval Prolongation (5.6) 4/2009

1 INDICATIONS AND USAGE

KALETRA is an HIV-1 protease inhibitor indicated in combination with other antiretroviral agents for the treatment of HIV-1 infection. (1)

2 DOSAGE AND ADMINISTRATION

Do not use once daily administration of KALETRA in:

● Therapy-experienced patients (2.1)
● Combination with efavirenz, nevirapine, (fos)amprenavir, or nelfinavir (2.1)
● Pediatric patients (2.2)

Tablets: May be taken with or without food, swallowed whole and not chewed, broken, or crushed. (2)
Oral Solution: Must be taken with food. (2)

ADULT PATIENTS Therapy-Naïve (2.1)
● 400/100 mg (two 200/50 mg tablets or 5 mL oral solution) twice daily or
● 800/200 mg (four 200/50 mg tablets or 10 mL oral solution) once daily.
ADULT PATIENTS Therapy-Experienced (2.1)
● 400/100 mg (two 200/50 mg tablets or 5 mL oral solution) twice daily

PEDIATRIC PATIENTS (ages 14 days and older) (2.2)

● Twice daily dose is based on body weight.

Concomitant Therapy in Adults and Pediatric Patients (2.1,2.2)

● Dose adjustments of KALETRA may be needed when co-administering with efavirenz, nevirapine, (fos)amprenavir, or nelfinavir.

3 DOSAGE FORMS AND STRENGTHS

● Film-coated tablets: 200 mg lopinavir and 50 mg ritonavir (3)

● Film-coated tablets: 100 mg lopinavir and 25 mg ritonavir (3)

● Oral solution: 80 mg lopinavir and 20 mg ritonavir per milliliter (3)

4 CONTRAINDICATIONS

Hypersensitivity to KALETRA (e.g., Stevens-Johnson syndrome, erythema multiforme) or any of its ingredients, including ritonavir. (4)

Coadministration with:
● drugs highly dependent on CYP3A for clearance and for which elevated plasma levels may result in serious and/or life-threatening events. (4)
● potent CYP3A inducers where significantly reduced lopinavir plasma concentrations may be associated with the potential for loss of virologic response and possible resistance and cross resistance. (4)

WARNINGS AND PRECAUTIONS

The following have been observed in patients receiving KALETRA:
● Drug Interactions: Consider drug-drug interaction potential to reduce risk of serious or life-threatening adverse reactions. (5.1)
● Pancreatitis: Fatalities have occurred; suspend therapy as clinically appropriate. (5.2)
● Hepatotoxicity: Fatalities have occurred. Monitor liver function before and during therapy, especially in patients with underlying hepatic disease, including hepatitis B and hepatitis C, or marked transaminase elevations.
(5.3, 8.6)
● PR interval prolongation may occur in some patients. Cases of second and third degree heart block have been reported. Use with caution in patients with preexisting conduction system disease, ischemic heart disease, cardiomyopathy, underlying structural heart disease or when administering with other drugs that may prolong the PR interval. (5.1, 5.5,12.3)
● QT interval prolongation and isolated cases of torsade de pointes have been reported although causality could not be established. Avoid use in patients with congenital long QT syndrome, those with hypokalemia, and with other drugs that prolong the QT interval. (5.1, 5.6,12.3)
● Patients may develop new onset or exacerbations of diabetes mellitus, hyperglycemia (5.4), immune reconstitution syndrome (5.7), redistribution/accumulation of body fat. (5.8)
● Total cholesterol and triglycerides elevations. Monitor prior to therapy and periodically thereafter. (5.9)
● Hemophilia: Spontaneous bleeding may occur, and additional factor VIII may be required. (5.10)

6 ADVERSE REACTIONS

The most common adverse reactions (> 5%) were diarrhea, nausea, abdominal pain, asthenia, vomiting, headache, and dyspepsia. (6.1, 6.2)

To report SUSPECTED ADVERSE REACTIONS, contact Abbott Laboratories at 1-800-633-9110 or FDA at 1-800-FDA-1088 or www.fda.gov/medwatch

7 DRUG INTERACTIONS

Coadministration of KALETRA can alter the concentrations of other drugs and other drugs may alter the concentrations of lopinavir. The potential for drug-drug interactions must be considered prior to and during therapy. (4, 5.1, 7, 12.3)

USE IN SPECIFIC POPULATIONS

● Pregnancy: Physicians are encouraged to register patients in the Antiretroviral Pregnancy Registry by calling 1-800-258-4263. (8.1)
● Pediatric Use: The safety, efficacy, and pharmacokinetic profiles of KALETRA in pediatric patients below the age of 14 days have not been established. (8.4)

FULL PRESCRIBING INFORMATION

1 INDICATIONS AND USAGE

KALETRA is indicated in combination with other antiretroviral agents for the treatment of HIV-1 infection.

The following points should be considered when initiating therapy with KALETRA:

- The use of other active agents with KALETRA is associated with a greater likelihood of treatment response [see Clinical Pharmacology (12.4) and Clinical Studies (14)].
- Genotypic or phenotypic testing and/or treatment history should guide the use of KALETRA [see Clinical Pharmacology (12.4)]. The number of baseline primary protease inhibitor mutations affects the virologic response to KALETRA [see Clinical Pharmacology (12.4)].
- Once daily administration of KALETRA is not recommended for therapy-experienced adult patients or any pediatric patients.

2 DOSAGE AND ADMINISTRATION

KALETRA tablets may be taken with or without food. The tablets should be swallowed whole and not chewed, broken, or crushed.

KALETRA oral solution must be taken with food.

2.1 Adult Patients

Therapy-Naïve Patients

- KALETRA tablets 400/100 mg (given as two 200/50 mg tablets) twice daily taken with or without food.
- KALETRA oral solution 400/100 mg (5 mL) twice daily taken with food.
- KALETRA tablets 800/200 mg (given as four 200/50 mg tablets) once daily taken with or without food.
- KALETRA oral solution 800/200 mg (10 mL) once daily taken with food.

Therapy-Experienced Patients

Once daily administration of KALETRA is not recommended in therapy-experienced patients.

- KALETRA tablets 400/100 mg (given as two 200/50 mg tablets) twice daily taken with or without food.
- KALETRA oral solution 400/100 mg (5 mL) twice daily taken with food.

Concomitant Therapy: Efavirenz, nevirapine, (fos)amprenavir or nelfinavir

[see Clinical Pharmacology (12.3) and Drug Interactions (7.3)]

KALETRA tablets and oral solution should not be administered as a once daily regimen in combination with efavirenz, nevirapine, (fos)amprenavir or nelfinavir.

- A dose increase is recommended for all patients who use KALETRA tablets. The recommended dose of KALETRA tablets is 500/125 mg (such as two 200/50 tablets and one 100/25 mg tablet) twice daily in combination with efavirenz, nevirapine, (fos)amprenavir or nelfinavir.
- A dose increase is recommended for all patients who use KALETRA oral solution. The recommended dose of KALETRA oral solution is 533/133 mg (6.5 mL) twice daily taken with food when used in combination with efavirenz, nevirapine, (fos)amprenavir or nelfinavir.

2.2 Pediatric Patients

KALETRA tablets and oral solution should not be administered once daily in pediatric patients < 18 years of age.

Healthcare professionals should pay special attention to accurate calculation of the dose of KALETRA, transcription of the medication order, dispensing information and dosing instructions to minimize the risk for medication errors, overdose, [see Overdosage (10)] and underdose.

Prescribers should calculate the appropriate dose of KALETRA for each individual child based on body weight (kg) or body surface area (BSA) and should not exceed the recommended adult dose.

Body surface area (BSA) can be calculated as follows:

The KALETRA dose can be calculated based on weight or BSA:

Based on Weight:

Patient Weight (kg) × Prescribed lopinavir dose (mg/kg) = Administered lopinavir dose (mg)

Based on BSA:

Patient BSA (m^2) × Prescribed lopinavir dose (mg/m^2) = Administered lopinavir dose (mg)

If KALETRA oral solution is used, the volume (mL) of KALETRA solution can be determined as follows:

Volume of KALETRA solution (mL) = Administered lopinavir dose (mg) ÷ 80 (mg/mL)

The dose of the oral solution should be administered using a calibrated dosing syringe.

Before prescribing KALETRA 100/25 mg tablets, children should be assessed for the ability to swallow intact tablets. If a child is unable to reliably swallow a KALETRA tablet, the KALETRA oral solution formulation should be prescribed.

14 Days to 6 Months:

In pediatric patients 14 days to 6 months of age, the recommended dosage of lopinavir/ritonavir using KALETRA oral solution is 16/4 mg/kg or 300/75 mg/m^2 twice daily. Prescribers should calculate the appropriate dose based on body weight or body surface area.

Because no data exists for dosage when administered with efavirenz, nevirapine, (fos)amprenavir, or nelfinavir, it is recommended that KALETRA not be administered in combination with these drugs in patients < 6 months of age.

6 Months to 18 Years:

Without Concomitant Efavirenz, Nevirapine, (Fos)amprenavir or Nelfinavir

In children 6 months to 18 years of age, the recommended dosage of lopinavir/ritonavir using KALETRA oral solution without concomitant efavirenz, nevirapine, (fos)amprenavir, or nelfinavir is 230/57.5 mg/m^2 given twice daily, not to exceed the recommended adult dose. If weight-based dosing is preferred, the recommended dosage of lopinavir/ritonavir for patients < 15 kg is 12/3 mg/kg given twice daily and the dosage for patients ≥ 15 kg to 40 kg is 10/2.5 mg/kg given twice daily.

Table 1 provides the dosing recommendations for pediatric patients 6 months to 18 years of age based on body weight or body surface area for KALETRA tablets.

Table 1. Pediatric Dosing Recommendations for Patients 6 Months to 18 Years of Age Based on Body Weight or Body Surface Area for KALETRA Tablets Without Concomitant Efavirenz, Nevirapine, (Fos)amprenavir, or Nelfinavir
Body Weight (kg) | Body Surface Area (m^2)* |  | Recommended number of 100/25 mg Tablets Twice Daily
15 to 25 |  | ≥0.6 to < 0.9 | 2
>25 to 35 |  | ≥0.9 to < 1.4 | 3
>35 |  | ≥1.4 | 4 (or two 200/50 mg tablets)
* KALETRA oral solution is available for children with a BSA less than 0.6 m^2 or those who are unable to reliably swallow a tablet.

Concomitant Therapy: Efavirenz, Nevirapine, (Fos)amprenavir, or Nelfinavir

A dose increase of KALETRA to 300/75 mg/m^2 is needed when co-administered with efavirenz, nevirapine, (fos)amprenavir, or nelfinavir in children (both treatment-naïve and treatment-experienced) 6 months to 18 years of age, not to exceed the recommended adult dose. If weight-based dosing is preferred, the recommended dosage for patients <15 kg is 13/3.25 mg/kg given twice daily and the dosage for patients >15 kg to 45 kg is 11/2.75 mg/kg given twice daily.

Table 2 provides the dosing recommendations for pediatric patients 6 months to 18 years of age based on body weight or body surface area for KALETRA tablets when given in combination with efavirenz, nevirapine, (fos)amprenavir, or nelfinavir.

Table 2. Pediatric Dosing Recommendations for Patients 6 Months to 18 Years of Age Based on Body Weight or Body Surface Area for KALETRA Tablets With Concomitant Efavirenz†, Nevirapine, (Fos)amprenavir† or Nelfinavir†
Body Weight (kg) | Body Surface Area (m^2)* |  | Recommended number of 100/25 mg Tablets Twice Daily
15 to 20 |  | ≥0.6 to < 0.8 | 2
>20 to 30 |  | ≥0.8 to < 1.2 | 3
>30 to 45 |  | ≥1.2 to <1.7 | 4 (or two 200/50 mg tablets)
>45 |  | ≥1.7 | 4 or 6 (or two or three 200/50 mg tablets) see Dosage and Administration, Adult Patients (2.1)
* KALETRA oral solution is available for children with a BSA less than 0.6 m^2 or those who are unable to reliably swallow a tablet.
† Please refer to the individual product labels for appropriate dosing in children.

3 DOSAGE FORMS AND STRENGTHS

● KALETRA Tablets, 200 mg lopinavir/50 mg ritonavir

Yellow, film-coated, ovaloid tablets debossed with the corporate Abbott “A” logo and the Abbo-Code KA providing 200 mg lopinavir/50 mg ritonavir.

● KALETRA Tablets, 100 mg lopinavir/25 mg ritonavir

Pale yellow, film-coated, ovaloid tablets debossed with the corporate Abbott “A” logo and the Abbo-Code KC providing 100 mg lopinavir/25 mg ritonavir.

● KALETRA Oral Solution

Light yellow to orange colored liquid containing 400 mg lopinavir/100 mg ritonavir per 5 mL (80 mg lopinavir/20 mg ritonavir per mL).

4 CONTRAINDICATIONS

● KALETRA is contraindicated in patients with previously demonstrated clinically significant hypersensitivity (e.g., Stevens-Johnson syndrome, erythema multiforme) to any of its ingredients, including ritonavir.

● Co-administration of KALETRA is contraindicated with drugs that are highly dependent on CYP3A for clearance and for which elevated plasma concentrations are associated with serious and/or life-threatening reactions.

● Co-administration of KALETRA is contraindicated with potent CYP3A inducers where significantly reduced lopinavir plasma concentrations may be associated with the potential for loss of virologic response and possible resistance and cross-resistance. These drugs are listed in Table 3.

Table 3. Drugs That Are Contraindicated With KALETRA
Drug Class | Drugs Within Class That Are Contraindicated With KALETRA | Clinical comments:
Antimycobacterial | Rifampin | May lead to loss of virologic response and possible resistance to KALETRA or to the class of protease inhibitors or other co-administered antiretroviral agents. [see Drug Interactions (7)]
Ergot Derivatives | Dihydroergotamine, ergonovine, ergotamine, methylergonovine | Potential for acute ergot toxicity characterized by peripheral vasospasm and ischemia of the extremities and other tissues.
GI motility agent | Cisapride | Potential for cardiac arrhythmias.
Herbal Products | St Johns wort (hypericum perforatum) | May lead to loss of virologic response and possible resistance to KALETRA or to the class of protease inhibitors.
HMG-CoA Reductase Inhibitors | Lovastatin, simvastatin | Potential for myopathy including rhabdomyolysis.
Neuroleptic | Pimozide | Potential for cardiac arrhythmias.
Sedative/Hypnotics | Triazolam; orally administered midazolama | Prolonged or increased sedation or respiratory depression.
a see Drug Interactions, Table 9 for parenterally administered midazolam

WARNINGS AND PRECAUTIONS

5.1 Drug Interactions

See Tables 3 and 9 for listing of drugs that are contraindicated for use with KALETRA due to potentially life-threatening adverse events, significant drug interactions, or loss of virologic activity [see Contraindications (4) and Drug Interactions (7)].

5.2 Pancreatitis

Pancreatitis has been observed in patients receiving KALETRA therapy, including those who developed marked triglyceride elevations. In some cases, fatalities have been observed. Although a causal relationship to KALETRA has not been established, marked triglyceride elevations are a risk factor for development of pancreatitis [see Warnings and Precautions (5.9)]. Patients with advanced HIV-1 disease may be at increased risk of elevated triglycerides and pancreatitis, and patients with a history of pancreatitis may be at increased risk for recurrence during KALETRA therapy.

Pancreatitis should be considered if clinical symptoms (nausea, vomiting, abdominal pain) or abnormalities in laboratory values (such as increased serum lipase or amylase values) suggestive of pancreatitis occur. Patients who exhibit these signs or symptoms should be evaluated and KALETRA and/or other antiretroviral therapy should be suspended as clinically appropriate.

5.3 Hepatotoxicity

Patients with underlying hepatitis B or C or marked elevations in transaminase prior to treatment may be at increased risk for developing or worsening of transaminase elevations or hepatic decompensation with use of KALETRA.

There have been postmarketing reports of hepatic dysfunction, including some fatalities. These have generally occurred in patients with advanced HIV-1 disease taking multiple concomitant medications in the setting of underlying chronic hepatitis or cirrhosis. A causal relationship with KALETRA therapy has not been established.

Appropriate laboratory testing should be conducted prior to initiating therapy with KALETRA and patients should be monitored closely during treatment. Increased AST/ALT monitoring should be considered in the patients with underlying chronic hepatitis or cirrhosis, especially during the first several months of KALETRA treatment [see Use In Specific Populations (8.6)].

5.4 Diabetes Mellitus/Hyperglycemia

New onset diabetes mellitus, exacerbation of pre-existing diabetes mellitus, and hyperglycemia have been reported during post-marketing surveillance in HIV-1 infected patients receiving protease inhibitor therapy. Some patients required either initiation or dose adjustments of insulin or oral hypoglycemic agents for treatment of these events. In some cases, diabetic ketoacidosis has occurred. In those patients who discontinued protease inhibitor therapy, hyperglycemia persisted in some cases. Because these events have been reported voluntarily during clinical practice, estimates of frequency cannot be made and a causal relationship between protease inhibitor therapy and these events has not been established.

5.5 PR Interval Prolongation

Lopinavir/ritonavir prolongs the PR interval in some patients. Cases of second or third degree atrioventricular block have been reported. KALETRA should be used with caution in patients with underlying structural heart disease, preexisting conduction system abnormalities, ischemic heart disease or cardiomyopathies, as these patients may be at increased risk for developing cardiac conduction abnormalities.

The impact on the PR interval of co-administration of KALETRA with other drugs that prolong the PR interval (including calcium channel blockers, beta-adrenergic blockers, digoxin and atazanavir) has not been evaluated. As a result, co-administration of KALETRA with these drugs should be undertaken with caution, particularly with those drugs metabolized by CYP3A. Clinical monitoring is recommended [see Clinical Pharmacology (12.3)].

5.6 QT Interval Prolongation

Postmarketing cases of QT interval prolongation and torsade de pointes have been reported although causality of KALETRA could not be established. Avoid use in patients with congenital long QT syndrome, those with hypokalemia, and with other drugs that prolong the QT interval [see Clinical Pharmacology (12.3)].

5.7 Immune Reconstitution Syndrome

Immune reconstitution syndrome has been reported in patients treated with combination antiretroviral therapy, including KALETRA. During the initial phase of combination antiretroviral treatment, patients whose immune system responds may develop an inflammatory response to indolent or residual opportunistic infections (such as Mycobacterium avium infection, cytomegalovirus, Pneumocystis jirovecii pneumonia [PCP], or tuberculosis) which may necessitate further evaluation and treatment.

5.8 Fat Redistribution

Redistribution/accumulation of body fat including central obesity, dorsocervical fat enlargement (buffalo hump), peripheral wasting, facial wasting, breast enlargement, and "cushingoid appearance" have been observed in patients receiving antiretroviral therapy. The mechanism and long-term consequences of these events are currently unknown. A causal relationship has not been established.

5.9 Lipid Elevations

Treatment with KALETRA has resulted in large increases in the concentration of total cholesterol and triglycerides [see Adverse Reactions (6.1)]. Triglyceride and cholesterol testing should be performed prior to initiating KALETRA therapy and at periodic intervals during therapy. Lipid disorders should be managed as clinically appropriate, taking into account any potential drug-drug interactions with KALETRA and HMG-CoA reductase inhibitors [see Contraindications (4) and Drug Interactions
(7.3)].

5.10 Patients with Hemophilia

Increased bleeding, including spontaneous skin hematomas and hemarthrosis have been reported in patients with hemophilia type A and B treated with protease inhibitors. In some patients additional factor VIII was given. In more than half of the reported cases, treatment with protease inhibitors was continued or reintroduced. A causal relationship between protease inhibitor therapy and these events has not been established.

5.11 Resistance/Cross-resistance

Because the potential for HIV cross-resistance among protease inhibitors has not been fully explored in KALETRA-treated patients, it is unknown what effect therapy with KALETRA will have on the activity of subsequently administered protease inhibitors [see Clinical Pharmacology (12.4)].

6 ADVERSE REACTIONS

The following adverse reactions are discussed in greater detail in other sections of the labeling.

- PR Interval Prolongation, QT Interval Prolongation [see Warnings and Precautions (5.5, 5.6)]
- Drug Interactions [see Warnings and Precautions (5.1)]
- Pancreatitis [see Warnings and Precautions (5.2)]
- Hepatotoxicity [see Warnings and Precautions (5.3)]

Because clinical trials are conducted under widely varying conditions, adverse reactions rates observed in the clinical trials of a drug cannot be directly compared to rates in the clinical trials of another drug and may not reflect the rates observed in practice.

6.1 Adults - Clinical Trials Experience

The safety profile of KALETRA in adults is primarily based on 1555 HIV-1 infected patients in clinical trials.

The most common adverse reaction was diarrhea, which was generally of mild to moderate severity. In study 730, the incidence of diarrhea of any severity during 48 weeks of therapy was 60% in patients receiving KALETRA tablets once daily compared to 57% in patients receiving KALETRA tablets twice daily. More patients receiving KALETRA tablets once daily (14, 4.2%) had ongoing diarrhea at the time of discontinuation as compared to patients receiving KALETRA tablets twice daily (6, 1.8%). In study 730, discontinuations due to any adverse reaction were 4.8% in patients receiving KALETRA tablets once daily as compared to 3% in patients receiving KALETRA tablets twice daily. In study 863, discontinuations of randomized therapy due to adverse reactions were 3.4% in KALETRA-treated and 3.7% in nelfinavir-treated patients.

Treatment-emergent clinical adverse reactions of moderate or severe intensity in ≥ 2% of patients treated with combination therapy for up to 48 weeks (Study 863 and 730) and for up to 360 weeks (Study 720) are presented in Table 4 (treatment-naïve patients); and for up to 48 weeks (Study 888), 84 weeks (Study 957) and 144 weeks (Study 765) in Table 5 (protease inhibitor experienced patients).

Table 4. Percentage of Adult Patients with Selected Treatment-Emergent^1 Adverse Reactions of Moderate or Severe Intensity Reported in ≥ 2% of Adult Antiretroviral-Naïve Patients
 | Study 863 (48 Weeks) |  | Study 720 (360 Weeks) | Study 730 (48 Weeks)
 | KALETRA 400/100 mg Twice Daily + d4T + 3TC (N = 326) | Nelfinavir 750 mg Three Times Daily + d4T + 3TC (N = 327) | KALETRA Twice Daily^2 + d4T + 3TC (N = 100) | KALETRA 800/200 mg Once Daily + TDF +FTC (N=333) | KALETRA 400/100 mg Twice Daily + TDF +FTC (N=331)
Endocrine Disorders
Hypogonadism | 0% | 0% | 2% | 0% | 0%
Gastrointestinal Disorders
Diarrhea | 16% | 17% | 28% | 17% | 15%
Nausea | 7% | 5% | 16% | 7% | 5%
Vomiting | 2% | 2% | 6% | 3% | 4%
Abdominal Pain | 4% | 3% | 11% | 1% | 1%
Dyspepsia | 2% | <1% | 6% | 0% | 0%
Flatulence | 2% | 1% | 4% | 1% | 1%
General Disorders and Administration Site Conditions
Asthenia | 4% | 3% | 9% | <1% | <1%
Infections and Infestations
Bronchitis | 0% | 0% | 2% | 0% | <1%
Investigations
Weight decreased | 1% | <1% | 2% | 0% | <1%
Metabolism and Nutrition Disorders
Anorexia | 1% | <1% | 2% | <1% | 1%
Musculoskeletal and Connective Tissue Disorders
Myalgia | 1% | 1% | 2% | 0% | 0%
Nervous System Disorders
Headache | 2% | 2% | 6% | 2% | 2%
Paresthesia | 1% | 1% | 2% | 0% | 0%
Psychiatric Disorders
Insomnia | 2% | 1% | 3% | 1% | 0%
Depression | 1% | 2% | 0% | 0% | 0%
Libido decreased | <1% | <1% | 2% | 0% | <1%
Skin and Subcutaneous Tissue Disorders
Rash | 1% | 2% | 5% | <1% | 1%
Vascular Disorders
Vasodilation | 0% | 0% | 3% | 0% | 0%
1 Includes adverse reactions of possible or probable relationship to study drug.
2 Includes adverse reaction data from dose group I (200/100 mg twice daily [N = 16] and 400/100 mg twice daily [N = 16]) and dose group II (400/100 mg twice daily [N = 35] and 400/200 mg twice daily [N = 33]). Within dosing groups, moderate to severe nausea of probable/possible relationship to KALETRA occurred at a higher rate in the 400/200 mg dose arm compared to the 400/100 mg dose arm in group II.
Definitions: d4T = Stavudine; 3TC = Lamivudine; TDF = Tenofovir Disoproxil Fumarate; FTC = Emtricitabine

Table 5. Percentage of Adult Patients with Selected Treatment-Emergent^1 Adverse Reactions of Moderate or Severe Intensity Reported in ≥ 2% of Adult Protease Inhibitor-Experienced Patients
 | Study 888 (48 Weeks) |  | Study 957^2 and Study 765^3 (84-144 Weeks)
 | KALETRA 400/100 mg Twice Daily + NVP + NRTIs (N = 148) | Investigator-selected protease inhibitor(s) + NVP + NRTIs (N = 140) | KALETRA Twice Daily + NNRTI + NRTIs (N = 127)
Gastrointestinal Disorders
Diarrhea | 7% | 9% | 23%
Nausea | 7% | 16% | 5%
Vomiting | 4% | 12% | 2%
Abdominal Pain | 2% | 2% | 4%
Dyspepsia | 1% | 1% | 2%
Flatulence | 1% | 2% | 2%
Dysphasia | 2% | 1% | 0%
General Disorders and Administration Site Conditions
Asthenia | 3% | 6% | 9%
Pyrexia | 2% | 1% | 2%
Chills | 2% | 0% | 0%
Investigations
Weight decreased | 0% | 1% | 3%
Metabolism and Nutrition Disorders
Anorexia | 1% | 3% | 0%
Musculoskeletal and Connective Tissue Disorders
Myalgia | 1% | 1% | 2%
Nervous System Disorders
Headache | 2% | 3% | 2%
Paresthesia | 1% | 0% | 2%
Psychiatric Disorders
Depression | 1% | 2% | 2%
Insomnia | 0% | 2% | 2%
Skin and Subcutaneous Tissue Disorders
Rash | 2% | 1% | 2%
Vascular Disorders
Hypertension | 0% | 0% | 2%
1 Includes adverse reactions of possible or probable relationship to study drug.
2 Includes adverse reaction data from patients receiving 400/100 mg twice daily (n = 29) or 533/133 mg Twice Daily (n = 28) for 84 weeks. Patients received KALETRA in combination with NRTIs and efavirenz.
3 Includes adverse reaction data from patients receiving 400/100 mg twice daily (n = 36) or 400/200 mg Twice Daily (n = 34) for 144 weeks. Patients received KALETRA in combination with NRTIs and nevirapine.
Definitions: NVP = Nevirapine; NRTI = Nucleoside Reverse Transcriptase Inhibitors; NNRTI = Non-nucleoside Reverse Transcriptase Inhibitors

Less Common Adverse Reactions

Treatment-emergent adverse reactions occurring in less than 2% of adult patients receiving KALETRA in the clinical trials supporting approval and of at least moderate intensity are listed below by system organ class.

Blood and Lymphatic System Disorders

Anemia, leukopenia, lymphadenopathy, and splenomegaly.

Cardiac Disorders

Atrial fibrillation, atrioventricular block, myocardial infarction, palpitation.

Ear and Labyrinth Disorders

Hyperacusis, tinnitus, and vertigo.

Endocrine Disorders

Cushing's syndrome and hypothyroidism.

Eye Disorders

Eye disorder and visual disturbance.

Gastrointestinal Disorders

Abdominal distension, abdominal pain upper, constipation, dry mouth, enteritis, enterocolitis, enterocolitis hemorrhagic, eructation, esophagitis, fecal incontinence, gastric disorder, gastritis, gastroesophageal reflux disease, hemorrhoids, mouth ulceration, pancreatitis, periodontitis, stomach discomfort, and stomatitis.

General Disorders and Administration Site Conditions

Chest pain, cyst, drug interaction, edema, edema peripheral, face edema, fatigue, hypertrophy, and malaise.

Hepatobiliary Disorders

Cholangitis, cholecystitis, cytolytic hepatitis, hepatic steatosis, hepatitis, hepatomegaly, jaundice, and liver tenderness.

Immune System Disorders

Drug hypersensitivity, hypersensitivity, and immune reconstitution syndrome.

Infections and Infestations

Bacterial infection, cellulitis, folliculitis, furuncle, gastroenteritis, influenza, otitis media, perineal abscess, pharyngitis, rhinitis, sialoadenitis, sinusitis, and viral infection.

Investigations

Drug level increased, glucose tolerance decreased, and weight increased.

Metabolism and Nutrition Disorders

Decreased appetite, dehydration, diabetes mellitus, hypovitaminosis, increased appetite, lactic acidosis, lipomatosis, and obesity.

Musculoskeletal and Connective Tissue Disorders

Arthralgia, arthropathy, back pain, muscular weakness, osteoarthritis, osteonecrosis, and pain in extremity.

Neoplasms Benign, Malignant and Unspecified (incl Cysts and Polyps)

Benign neoplasm of skin, lipoma, and neoplasm.

Nervous System Disorders

Ageusia, amnesia, ataxia, cerebral infarction, convulsion, dizziness, dysgeusia, dyskinesia, encephalopathy, extrapyramidal disorder, facial palsy, hypertonia, migraine, neuropathy, neuropathy peripheral, somnolence, and tremor.

Psychiatric Disorders

Abnormal dreams, affect lability, agitation, anxiety, apathy, confusional state, nervousness, and thinking abnormal.

Renal and Urinary Disorders

Nephritis, nephrolithiasis, renal disorder, and urine abnormality.

Reproductive System and Breast Disorders

Breast enlargement, ejaculation disorder, erectile dysfunction, and gynecomastia.

Respiratory, Thoracic and Mediastinal Disorders

Asthma, cough, dyspnea, and pulmonary edema.

Skin and Subcutaneous Tissue Disorders

Acne, alopecia, dermatitis acneiform, dermatitis allergic, dermatitis exfoliative, dry skin, eczema, hyperhidrosis, idiopathic capillaritis, nail disorder, pruritis, rash generalized, rash maculo-papular, seborrhea, skin discoloration, skin hypertrophy, skin striae, skin ulcer, and swelling face.

Vascular Disorders

Deep vein thrombosis, orthostatic hypotension, thrombophlebitis, varicose vein, and vasculitis.

Laboratory Abnormalities

The percentages of adult patients treated with combination therapy with Grade 3-4 laboratory abnormalities are presented in Table 6 (treatment-naïve patients) and Table 7 (treatment-experienced patients).

Table 6. Grade 3-4 Laboratory Abnormalities Reported in ≥ 2% of Adult Antiretroviral-Naïve Patients
 |  | Study 863 (48 Weeks) |  | Study 720 (360 Weeks) | Study 730 (48 Weeks)
Variable | Limit^1 | KALETRA 400/100 mg Twice Daily + d4T +3TC (N = 326) | Nelfinavir 750 mg Three Times Daily + d4T + 3TC (N = 327) | KALETRA Twice Daily + d4T + 3TC (N = 100) | KALETRA Once Daily + TDF +FTC (N=333) | KALETRA Twice Daily + TDF +FTC (N=331)
Chemistry | High
Glucose | > 250 mg/dL | 2% | 2% | 4% | 0% | <1%
Uric Acid | > 12 mg/dL | 2% | 2% | 5% | <1% | 1%
SGOT/ AST^2 | > 180 U/L | 2% | 4% | 10% | 1% | 2%
SGPT/ ALT^2 | >215 U/L | 4% | 4% | 11% | 1% | 1%
GGT | >300 U/L | N/A | N/A | 10% | N/A | N/A
Total Cholesterol | >300 mg/dL | 9% | 5% | 27% | 4% | 3%
Triglycerides | >750 mg/dL | 9% | 1% | 29% | 3% | 6%
Amylase | >2 x ULN | 3% | 2% | 4% | N/A | N/A
Lipase | >2 x ULN | N/A | N/A | N/A | 3% | 5%
Chemistry | Low
Calculated Creatinine Clearance | <50 mL/min | N/A | N/A | N/A | 2% | 2%
Hematology | Low
Neutrophils | <0.75 x 10^9/L | 1% | 3% | 5% | 2% | 1%
1 ULN = upper limit of the normal range; N/A = Not Applicable.
2 Criterion for Study 730 was >5x ULN (AST/ALT).

Table 7. Grade 3-4 Laboratory Abnormalities Reported in ≥ 2% of Adult Protease Inhibitor-Experienced Patients
 |  | Study 888 (48 Weeks) |  | Study 957^2 and Study 765^3 (84-144 Weeks)
Variable | Limit^1 | KALETRA 400/100 mg Twice Daily + NVP + NRTIs (N = 148) | Investigator-selected protease inhibitor(s) + NVP + NRTIs (N = 140) | KALETRA Twice Daily + NNRTI + NRTIs (N = 127)
Chemistry | High
Glucose | >250 mg/dL | 1% | 2% | 5%
Total Bilirubin | >3.48 mg/dL | 1% | 3% | 1%
SGOT/AST | >180 U/L | 5% | 11% | 8%
SGPT/ALT | >215 U/L | 6% | 13% | 10%
GGT | >300 U/L | N/A | N/A | 29%
Total Cholesterol | >300 mg/dL | 20% | 21% | 39%
Triglycerides | >750 mg/dL | 25% | 21% | 36%
Amylase | >2 x ULN | 4% | 8% | 8%
Chemistry | Low
Inorganic Phosphorus | <1.5 mg/dL | 1% | 0% | 2%
Hematology | Low
Neutrophils | <0.75 x 10^9/L | 1% | 2% | 4%
1 ULN = upper limit of the normal range; N/A = Not Applicable.
2 Includes clinical laboratory data from patients receiving 400/100 mg twice daily (n = 29) or 533/133 mg twice daily (n = 28) for 84 weeks. Patients received KALETRA in combination with NRTIs and efavirenz.
3 Includes clinical laboratory data from patients receiving 400/100 mg twice daily (n = 36) or 400/200 mg twice daily (n = 34) for 144 weeks. Patients received KALETRA in combination with NRTIs and nevirapine.

6.2 Pediatric Patients - Clinical Trials Experience

KALETRA oral solution dosed up to 300/75 mg/m^2 has been studied in 100 pediatric patients 6 months to 12 years of age. The adverse reaction profile seen during Study 940 was similar to that for adult patients.

Dysgeusia (22%), vomiting (21%), and diarrhea (12%) were the most common adverse reactions of any severity reported in pediatric patients treated with combination therapy for up to 48 weeks in Study 940. A total of 8 patients experienced adverse reactions of moderate to severe intensity. The adverse reactions meeting these criteria and reported for the 8 subjects include: hypersensitivity (characterized by fever, rash and jaundice), pyrexia, viral infection, constipation, hepatomegaly, pancreatitis, vomiting, alanine aminotransferase increased, dry skin, rash, and dysgeusia. Rash was the only event of those listed that occurred in 2 or more subjects (N = 3).

KALETRA oral solution dosed at 300/75 mg/m^2 has been studied in 31 pediatric patients 14 days to 6 months of age. The adverse reaction profile in Study 1030 was similar to that observed in older children and adults. No adverse reaction was reported in greater than 10% of subjects. Adverse drug reactions of moderate to severe intensity occurring in 2 or more subjects included decreased neutrophil count (N=3), anemia (N=2), high potassium (N=2), and low sodium (N=2).

KALETRA oral solution and soft gelatin capsules dosed at higher than recommended doses including 400/100 mg/m^2 (without concomitant NNRTI) and 480/120 mg/m^2 (with concomitant NNRTI) have been studied in 26 pediatric patients 7 to 18 years of age in Study 1038. Patients also had saquinavir mesylate added to their regimen at Week 4. Rash (12%), blood cholesterol abnormal (12%) and blood triglycerides abnormal (12%) were the only adverse reactions reported in greater than 10% of subjects. Adverse drug reactions of moderate to severe intensity occurring in 2 or more subjects included rash (N=3), blood triglycerides abnormal (N=3), and electrocardiogram QT prolonged (N=2). Both subjects with QT prolongation had additional predisposing conditions such as electrolyte abnormalities, concomitant medications, or pre-existing cardiac abnormalities.

Laboratory Abnormalities

The percentages of pediatric patients treated with combination therapy including KALETRA with Grade 3-4 laboratory abnormalities are presented in Table 8.

Table 8. Grade 3-4 Laboratory Abnormalities Reported in ≥ 2% Pediatric Patients in Study 940
Variable | Limit^1 | KALETRA Twice Daily + RTIs (N = 100)
Chemistry | High
Sodium | > 149 mEq/L | 3%
Total Bilirubin | ≥ 3.0 x ULN | 3%
SGOT/AST | > 180 U/L | 8%
SGPT/ALT | > 215 U/L | 7%
Total Cholesterol | > 300 mg/dL | 3%
Amylase | > 2.5 x ULN | 7%^2
Chemistry | Low
Sodium | < 130 mEq/L | 3%
Hematology | Low
Platelet Count | < 50 x 10^9/L | 4%
Neutrophils | < 0.40 x 10^9/L | 2%
1 ULN = upper limit of the normal range.
2 Subjects with Grade 3-4 amylase confirmed by elevations in pancreatic amylase.

6.3 Postmarketing Experience

The following adverse reactions have been reported during postmarketing use of KALETRA. Because these reactions are reported voluntarily from a population of unknown size, it is not possible to reliably estimate their frequency or establish a causal relationship to KALETRA exposure.

Body as a Whole
Redistribution/accumulation of body fat has been reported [see Warnings and Precautions (5.8)].

Cardiovascular
Bradyarrhythmias. First–degree AV block, second-degree AV block, third-degree AV block, QTc interval prolongation, torsades (torsade) de pointes [see Warnings and Precautions (5.5,5.6)].

Skin and Appendages
Stevens Johnson Syndrome and erythema multiforme.

7 DRUG INTERACTIONS

See also Contraindications (4), Clinical Pharmacology (12.3)

7.1 Potential for KALETRA to Affect Other Drugs

Lopinavir/ritonavir is an inhibitor of CYP3A and may increase plasma concentrations of agents that are primarily metabolized by CYP3A. Agents that are extensively metabolized by CYP3A and have high first pass metabolism appear to be the most susceptible to large increases in AUC (> 3-fold) when co-administered with KALETRA. Thus, co-administration of KALETRA with drugs highly dependent on CYP3A for clearance and for which elevated plasma concentrations are associated with serious and/or life-threatening events is contraindicated. Co-administration with other CYP3A substrates may require a dose adjustment or additional monitoring as shown in Table 9.

Additionally, KALETRA induces glucuronidation.

7.2 Potential For Other Drugs To Affect Lopinavir

Lopinavir/ritonavir is a CYP3A substrate; therefore, drugs that induce CYP3A may decrease lopinavir plasma concentrations and reduce KALETRA’s therapeutic effect. Although not observed in the KALETRA/ketoconazole drug interaction study, co-administration of KALETRA and other drugs that inhibit CYP3A may increase lopinavir plasma concentrations.

7.3 Established and Other Potentially Significant Drug Interactions

Table 9 provides a listing of established or potentially clinically significant drug interactions. Alteration in dose or regimen may be recommended based on drug interaction studies or predicted interaction [see Clinical Pharmacology (12.3) for magnitude of interaction].

Table 9. Established and Other Potentially Significant Drug Interactions
Concomitant Drug Class: Drug Name | Effect on Concentration of Lopinavir or Concomitant Drug | Clinical Comment
HIV-1 Antiviral Agents
Non-nucleoside Reverse Transcriptase Inhibitors: efavirenz*, nevirapine* | ↓ lopinavir | KALETRA dose increase is recommended in all patients [see Dosage and Administration (2.1) and Clinical Pharmacology (12.3)]. Increasing the dose of KALETRA tablets to 500/125 mg (given as two 200/50 mg tablets and one 100/25 mg tablet) twice daily co-administered with efavirenz resulted in similar lopinavir concentrations compared to KALETRA tablets 400/100 mg (given as two 200/50 mg tablets) twice daily without efavirenz. Increasing the dose of KALETRA tablets to 600/150 mg (given as three 200/50 mg tablets) twice daily co-administered with efavirenz resulted in significantly higher lopinavir plasma concentrations compared to KALETRA tablets 400/100 mg twice daily without efavirenz. KALETRA should not be administered once daily in combination with efavirenz or nevirapine. [see Dosage and Administration (2.1) and Clinical Pharmacology (12.3)].
Non-nucleoside Reverse Transcriptase Inhibitor: delavirdine | ↑ lopinavir | Appropriate doses of the combination with respect to safety and efficacy have not been established.
Nucleoside Reverse Transcriptase Inhibitor: didanosine |  | KALETRA tablets can be administered simultaneously with didanosine without food. For KALETRA oral solution, it is recommended that didanosine be administered on an empty stomach; therefore, didanosine should be given one hour before or two hours after KALETRA oral solution (given with food).
Nucleoside Reverse Transcriptase Inhibitor: tenofovir | ↑ tenofovir | KALETRA increases tenofovir concentrations. The mechanism of this interaction is unknown. Patients receiving KALETRA and tenofovir should be monitored for adverse reactions associated with tenofovir.
Nucleoside Reverse Transcriptase Inhibitor: abacavir zidovudine | ↓ abacavir ↓ zidovudine | KALETRA induces glucuronidation; therefore, KALETRA has the potential to reduce zidovudine and abacavir plasma concentrations. The clinical significance of this potential interaction is unknown.
HIV-1 Protease Inhibitor: amprenavir* | ↑ amprenavir ↓ lopinavir | KALETRA should not be administered once daily in combination with amprenavir. [see Dosage and Administration (2.1)].
HIV-1 Protease Inhibitor: fosamprenavir/ritonavir | ↓ amprenavir ↓ lopinavir | An increased rate of adverse reactions has been observed with co-administration of these medications. Appropriate doses of the combinations with respect to safety and efficacy have not been established.
HIV-1 Protease Inhibitor: indinavir* | ↑ indinavir | Decrease indinavir dose to 600 mg twice daily, when co-administered with KALETRA 400/100 mg twice daily [see Clinical Pharmacology (12.3)]. KALETRA once daily has not been studied in combination with indinavir.
HIV-1 Protease Inhibitor: nelfinavir* | ↑ nelfinavir ↑ M8 metabolite of nelfinavir ↓ lopinavir | KALETRA should not be administered once daily in combination with nelfinavir. [see Dosage and Administration (2.1) and Clinical Pharmacology (12.3)].
HIV-1 Protease Inhibitor: ritonavir* | ↑ lopinavir | Appropriate doses of additional ritonavir in combination with KALETRA with respect to safety and efficacy have not been established.
HIV-1 Protease Inhibitor: saquinavir* | ↑ saquinavir | The saquinavir dose is 1000 mg twice daily, when co-administered with KALETRA 400/100 mg twice daily. KALETRA once daily has not been studied in combination with saquinavir.
HIV-1 Protease Inhibitor: tipranavir | ↓ lopinavir AUC and Cmin | KALETRA should not be administered with tipranavir (500 mg twice daily) co-administered with ritonavir (200 mg twice daily).
HIV CCR5 – antagonist: maraviroc | ↑ maraviroc | Concurrent administration of maraviroc with KALETRA will increase plasma levels of maraviroc. When co-administered, patients should receive 150 mg twice daily of maraviroc. For further details see complete prescribing information for Selzentry® (maraviroc).
Other Agents
Antiarrhythmics: amiodarone, bepridil, lidocaine (systemic), and quinidine | ↑ antiarrhythmics | Caution is warranted and therapeutic concentration monitoring (if available) is recommended for antiarrhythmics when co-administered with KALETRA.
Anticancer Agents: vincristine vinblastine | ↑ anticancer agents | Concentrations of vincristine or vinblastine may be increased when co-administered with lopinavir/ritonavir (KALETRA) resulting in the potential for increased adverse events usually associated with these anticancer agents. Consideration should be given to temporarily withholding the ritonavir-containing antiretroviral regimen in patients who develop significant hematologic or gastrointestinal side effects when lopinavir/ritonavir (KALETRA) is administered concurrently with vincristine or vinblastine. If the antiretroviral regimen must be withheld for a prolonged period, consideration should be given to initiating a revised regimen that does not include a CYP3A or P-gp inhibitor.
Anticoagulant: warfarin |  | Concentrations of warfarin may be affected. It is recommended that INR (international normalized ratio) be monitored.
Anticonvulsants: carbamazepine, phenobarbital, phenytoin | ↓ lopinavir ↓ phenytoin | KALETRA may be less effective due to decreased lopinavir plasma concentrations in patients taking these agents concomitantly and should be used with caution. KALETRA should not be administered once daily in combination with carbamazepine, phenobarbital, or phenytoin. In addition, co-administration of phenytoin and KALETRA may cause decreases in steady-state phenytoin concentrations. Phenytoin levels should be monitored when co-administering with KALETRA.
Antidepressant: bupropion | ↓ bupropion ↓ active metabolite, hydroxybupropion | Concurrent administration of bupropion with KALETRA may decrease plasma levels of both bupropion and its active metabolite (hydroxybupropion). Patients receiving KALETRA and bupropion concurrently should be monitored for an adequate clinical response to bupropion.
Antidepressant: trazodone | ↑ trazodone | Concomitant use of trazodone and KALETRA may increase concentrations of trazodone. Adverse reactions of nausea, dizziness, hypotension and syncope have been observed following co-administration of trazodone and ritonavir. If trazodone is used with a CYP3A4 inhibitor such as ritonavir, the combination should be used with caution and a lower dose of trazodone should be considered.
Anti-infective: clarithromycin | ↑ clarithromycin | For patients with renal impairment, the following dosage adjustments should be considered:; - For patients with CLCR 30 to 60 mL/min the dose of clarithromycin should be reduced by 50%. - For patients with CLCR < 30 mL/min the dose of clarithromycin should be decreased by 75%.; No dose adjustment for patients with normal renal function is necessary.
Antifungals: ketoconazole*, itraconazole, voriconazole | ↑ ketoconazole ↑ itraconazole ↓ voriconazole | High doses of ketoconazole (>200 mg/day) or itraconazole (> 200 mg/day) are not recommended. Co-administration of voriconazole with KALETRA has not been studied. However, a study has been shown that administration of voriconazole with ritonavir 100 mg every 12 hours decreased voriconazole steady-state AUC by an average of 39%; therefore, co-administration of KALETRA and voriconazole may result in decreased voriconazole concentrations and the potential for decreased voriconazole effectiveness and should be avoided, unless an assessment of the benefit/risk to the patient justifies the use of voriconazole. Otherwise, alternative antifungal therapies should be considered in these patients.
Antimycobacterial: rifabutin* | ↑ rifabutin and rifabutin metabolite | Dosage reduction of rifabutin by at least 75% of the usual dose of 300 mg/day is recommended (i.e., a maximum dose of 150 mg every other day or three times per week). Increased monitoring for adverse reactions is warranted in patients receiving the combination. Further dosage reduction of rifabutin may be necessary.
Antimycobacterial: rifampin | ↓ lopinavir | May lead to loss of virologic response and possible resistance to KALETRA or to the class of protease inhibitors or other co-administered antiretroviral agents. A study evaluated combination of rifampin 600 mg once daily, with KALETRA 800/200 mg twice daily or KALETRA 400/100 mg + ritonavir 300 mg twice daily. Pharmacokinetic and safety results from this study do not allow for a dose recommendation. Nine subjects (28%) experienced a ≥ grade 2 increase in ALT/AST, of which seven (21%) prematurely discontinued study per protocol. Based on the study design, it is not possible to determine whether the frequency or magnitude of the ALT/AST elevations observed is higher than what would be seen with rifampin alone. [see Clinical Pharmacology (12.3) for magnitude of interaction].
Antiparasitic: atovaquone | ↓ atovaquone | Clinical significance is unknown; however, increase in atovaquone doses may be needed.
Benzodiazepines: parenterally administered midazolam | ↑ midazolam | Midazolam is extensively metabolized by CYP3A4. Increases in the concentration of midazolam are expected to be significantly higher with oral than parenteral administration. Therefore, KALETRA should not be given with orally administered midazolam [see Contraindications (4)]. If KALETRA is coadministered with parenteral midazolam, close clinical monitoring for respiratory depression and/or prolonged sedation should be exercised and dosage adjustment should be considered.
Calcium Channel Blockers, dihydropyridine: e.g., felodipine, nifedipine, nicardipine | ↑ dihydropyridine calcium channel blockers | Caution is warranted and clinical monitoring of patients is recommended.
Corticosteroid: dexamethasone | ↓ lopinavir | Use with caution. KALETRA may be less effective due to decreased lopinavir plasma concentrations in patients taking these agents concomitantly.
disulfiram/metronidazole |  | KALETRA oral solution contains alcohol, which can produce disulfiram-like reactions when co-administered with disulfiram or other drugs that produce this reaction (e.g., metronidazole).
PDE5 inhibitors: sildenafil, tadalafil, vardenafil | ↑ sildenafil ↑ tadalafil ↑ vardenafil | Particular caution should be used when prescribing sildenafil, tadalafil, or vardenafil in patients receiving KALETRA. Co-administration of KALETRA with these drugs is expected to substantially increase their concentrations and may result in an increase in associated adverse reactions including hypotension, syncope, visual changes and prolonged erection. It is recommended not to exceed the following doses:; - Sildenafil: 25 mg every 48 hours - Tadalafil: 10 mg every 72 hours - Vardenafil: 2.5 mg every 72 hours
HMG-CoA Reductase Inhibitors: atorvastatin rosuvastatin | ↑ atorvastatin ↑ rosuvastatin | Use lowest possible dose of atorvastatin or rosuvastatin with careful monitoring, or consider other HMG-CoA reductase inhibitors such as pravastatin or fluvastatin in combination with KALETRA.
Immunosuppressants: cyclosporine, tacrolimus, rapamycin | ↑ immunosuppressants | Therapeutic concentration monitoring is recommended for immunosuppressant agents when co-administered with KALETRA.
Inhaled Steroid: fluticasone | ↑ fluticasone | Concomitant use of fluticasone propionate and KALETRA may increase plasma concentrations of fluticasone propionate, resulting in significantly reduced serum cortisol concentrations. Systemic corticosteroid effects including Cushing's syndrome and adrenal suppression have been reported during post-marketing use in patients receiving ritonavir and inhaled or intranasally administered fluticasone propionate. Co-administration of fluticasone propionate and KALETRA is not recommended unless the potential benefit to the patient outweighs the risk of systemic corticosteroid side effect.
Narcotic Analgesic: methadone* | ↓ methadone | Dosage of methadone may need to be increased when co-administered with KALETRA.
Contraceptive: ethinyl estradiol* | ↓ ethinyl estradiol | Because contraceptive steroid concentrations may be altered when KALETRA is co-administered with oral contraceptives or with the contraceptive patch, alternative methods of nonhormonal contraception are recommended.
* see Clinical Pharmacology (12.3) for Magnitude of Interaction.

7.4 Drugs with No Observed or Predicted Interactions with KALETRA

Drug interaction studies reveal no clinically significant interaction between KALETRA and desipramine (CYP2D6 probe), pravastatin, stavudine, lamivudine, omeprazole or ranitidine.

Based on known metabolic profiles, clinically significant drug interactions are not expected between KALETRA and fluvastatin, dapsone, trimethoprim/sulfamethoxazole, azithromycin, erythromycin, or fluconazole.

USE IN SPECIFIC POPULATIONS

8.1 Pregnancy

Pregnancy Category C.

No treatment-related malformations were observed when lopinavir in combination with ritonavir was administered to pregnant rats or rabbits. Embryonic and fetal developmental toxicities (early resorption, decreased fetal viability, decreased fetal body weight, increased incidence of skeletal variations and skeletal ossification delays) occurred in rats at a maternally toxic dosage. Based on AUC measurements, the drug exposures in rats at the toxic doses were approximately 0.7-fold for lopinavir and 1.8-fold for ritonavir for males and females that of the exposures in humans at the recommended therapeutic dose (400/100 mg twice daily). In a peri- and postnatal study in rats, a developmental toxicity (a decrease in survival in pups between birth and postnatal Day 21) occurred.

No embryonic and fetal developmental toxicities were observed in rabbits at a maternally toxic dosage. Based on AUC measurements, the drug exposures in rabbits at the toxic doses were approximately 0.6-fold for lopinavir and 1.0-fold for ritonavir that of the exposures in humans at the recommended therapeutic dose (400/100 mg twice daily). There are, however, no adequate and well-controlled studies in pregnant women. KALETRA should be used during pregnancy only if the potential benefit justifies the potential risk to the fetus.

Antiretroviral Pregnancy Registry: To monitor maternal-fetal outcomes of pregnant women exposed to KALETRA, an Antiretroviral Pregnancy Registry has been established. Physicians are encouraged to register patients by calling 1-800-258-4263.

8.3 Nursing Mothers

The Centers for Disease Control and Prevention recommend that HIV-1 infected mothers not breast-feed their infants to avoid risking postnatal transmission of HIV-1. Studies in rats have demonstrated that lopinavir is secreted in milk. It is not known whether lopinavir is secreted in human milk. Because of both the potential for HIV-1 transmission and the potential for serious adverse reactions in nursing infants, mothers should be instructed not to breast-feed if they are receiving KALETRA.

8.4 Pediatric Use

The safety, efficacy, and pharmacokinetic profiles of KALETRA in pediatric patients below the age of 14 days have not been established. KALETRA once daily has not been evaluated in pediatric patients.

An open-label, multi-center, dose-finding trial was performed to evaluate the pharmacokinetic profile, tolerability, safety and efficacy of KALETRA oral solution containing lopinavir 80 mg/mL and ritonavir 20 mg/mL at a dose of with 300/75 mg/m^2 twice daily plus two NRTIs in HIV-infected infants ≥14 days and < 6 months of age. Results revealed that infants younger than 6 months of age generally had lower lopinavir AUC12 than older children (6 months to 12 years of age), however, despite the lower lopinavir drug exposure observed, antiviral activity was demonstrated as reflected in the proportion of subjects who achieved HIV-RNA <400 copies/mL at Week 24 [see Adverse Reactions (6.2), Clinical Pharmacology (12.3), Clinical Studies (14.4)].

Safety and efficacy in pediatric patients > 6 months of age was demonstrated in a clinical trial in 100 patients. The clinical trial was an open-label, multicenter trial evaluating the pharmacokinetic profile, tolerability, safety, and efficacy of KALETRA oral solution containing lopinavir 80 mg/mL and ritonavir 20 mg/mL in 100 antiretroviral naïve and experienced pediatric patients ages 6 months to 12 years. Dose selection for patients 6 months to 12 years of age was based on the following results. The 230/57.5 mg/m^2 oral solution twice daily regimen without nevirapine and the 300/75 mg/m^2 oral solution twice daily regimen with nevirapine provided lopinavir plasma concentrations similar to those obtained in adult patients receiving the 400/100 mg twice daily regimen (without nevirapine) [see Adverse Reactions (6.2), Clinical Pharmacology (12.3), Clinical Studies (14.4)].

A prospective multicenter, open-label trial evaluated the pharmacokinetic profile, tolerability, safety and efficacy of high-dose KALETRA with or without concurrent NNRTI therapy (Group 1: 400/100 mg/m^2 twice daily + ≥ 2 NRTIs; Group 2: 480/120 mg/m^2 twice daily + ≥ 1 NRTI + 1 NNRTI) in children and adolescents ≥ 2 years to < 18 years of age who had failed prior therapy. Patients also had saquinavir mesylate added to their regimen. This strategy was intended to assess whether higher than approved doses of KALETRA could overcome protease inhibitor cross-resistance. High doses of KALETRA exhibited a safety profile similar to those observed in previous trials; changes in HIV-1 RNA were less than anticipated; three patients had HIV-1 RNA <400 copies/mL at Week 48. CD4+ cell count increases were noted in the eight patients who remained on treatment for 48 weeks [see Adverse Reactions (6.2), Clinical Pharmacology (12.3)].

8.5 Geriatric Use

Clinical studies of KALETRA did not include sufficient numbers of subjects aged 65 and over to determine whether they respond differently from younger subjects. In general, appropriate caution should be exercised in the administration and monitoring of KALETRA in elderly patients reflecting the greater frequency of decreased hepatic, renal, or cardiac function, and of concomitant disease or other drug therapy.

8.6 Hepatic Impairment

KALETRA is principally metabolized by the liver; therefore, caution should be exercised when administering this drug to patients with hepatic impairment, because lopinavir concentrations may be increased [see Warnings and Precautions (5.3) and Clinical Pharmacology (12.3)].

10 OVERDOSAGE

Overdoses with KALETRA oral solution have been reported. One of these reports described fatal cardiogenic shock in a 2.1 kg infant who received a single dose of 6.5 mL of KALETRA oral solution nine days prior. However, a causal relationship between the overdose and the outcome could not be established. Healthcare professionals should be aware that KALETRA oral solution is highly concentrated and therefore, should pay special attention to accurate calculation of the dose of KALETRA, transcription of the medication order, dispensing information and dosing instructions to minimize the risk for medication errors and overdose. This is especially important for infants and young children.

KALETRA oral solution contains 42.4% alcohol (v/v). Accidental ingestion of the product by a young child could result in significant alcohol-related toxicity and could approach the potential lethal dose of alcohol.

Human experience of acute overdosage with KALETRA is limited. Treatment of overdose with KALETRA should consist of general supportive measures including monitoring of vital signs and observation of the clinical status of the patient. There is no specific antidote for overdose with KALETRA. If indicated, elimination of unabsorbed drug should be achieved by emesis or gastric lavage. Administration of activated charcoal may also be used to aid in removal of unabsorbed drug. Since KALETRA is highly protein bound, dialysis is unlikely to be beneficial in significant removal of the drug.

11 DESCRIPTION

KALETRA (lopinavir/ritonavir) is a co-formulation of lopinavir and ritonavir. Lopinavir is an inhibitor of the HIV-1 protease. As co-formulated in KALETRA, ritonavir inhibits the CYP3A-mediated metabolism of lopinavir, thereby providing increased plasma levels of lopinavir.

Lopinavir is chemically designated as [1S-[1R*,(R*), 3R*, 4R*]]-N-[4-[[(2,6-dimethylphenoxy)acetyl]amino]-3-hydroxy-5-phenyl-1-(phenylmethyl)pentyl]tetrahydro-alpha-(1-methylethyl)-2-oxo-1(2H)-pyrimidineacetamide. Its molecular formula is C37H48N4O5, and its molecular weight is 628.80. Lopinavir is a white to light tan powder. It is freely soluble in methanol and ethanol, soluble in isopropanol and practically insoluble in water. Lopinavir has the following structural formula:

Ritonavir is chemically designated as 10-hydroxy-2-methyl-5-(1-methylethyl)-1- [2-(1-methylethyl)-4-thiazolyl]-3,6-dioxo-8,11-bis(phenylmethyl)-2,4,7,12-tetraazatridecan-13-oic acid, 5-thiazolylmethyl ester, [5S-(5R*,8R*,10R*,11R*)]. Its molecular formula is C37H48N6O5S2, and its molecular weight is 720.95. Ritonavir is a white to light tan powder. It is freely soluble in methanol and ethanol, soluble in isopropanol and practically insoluble in water. Ritonavir has the following structural formula:

KALETRA film-coated tablets are available for oral administration in two strengths:

- Yellow tablets containing 200 mg of lopinavir and 50 mg of ritonavir
- Pale yellow tablets containing 100 mg of lopinavir and 25 mg of ritonavir.

The yellow, 200 mg lopinavir/50 mg ritonavir, tablets contain the following inactive ingredients: copovidone, sorbitan monolaurate, colloidal silicon dioxide, and sodium stearyl fumarate. The following are the ingredients in the film coating: hypromellose, titanium dioxide, polyethylene glycol 400, hydroxypropyl cellulose, talc, colloidal silicon dioxide, polyethylene glycol 3350, yellow ferric oxide E172, and polysorbate 80.

The pale yellow, 100 mg lopinavir/25 mg ritonavir, tablets contain the following inactive ingredients: copovidone, sorbitan monolaurate, colloidal silicon dioxide, and sodium stearyl fumarate. The following are the ingredients in the film coating: polyvinyl alcohol, titanium dioxide, talc, polyethylene glycol 3350, and yellow ferric oxide E172.

KALETRA oral solution is available for oral administration as 80 mg lopinavir and 20 mg ritonavir per milliliter with the following inactive ingredients: acesulfame potassium, alcohol, artificial cotton candy flavor, citric acid, glycerin, high fructose corn syrup, Magnasweet-110 flavor, menthol, natural & artificial vanilla flavor, peppermint oil, polyoxyl 40 hydrogenated castor oil, povidone, propylene glycol, saccharin sodium, sodium chloride, sodium citrate, and water.

KALETRA oral solution contains 42.4% alcohol (v/v).

12 CLINICAL PHARMACOLOGY

12.1 Mechanism of Action

Lopinavir is an antiviral drug [see Clinical Pharmacology (12.4)].

12.3 Pharmacokinetics

The pharmacokinetic properties of lopinavir co-administered with ritonavir have been evaluated in healthy adult volunteers and in HIV-1 infected patients; no substantial differences were observed between the two groups. Lopinavir is essentially completely metabolized by CYP3A. Ritonavir inhibits the metabolism of lopinavir, thereby increasing the plasma levels of lopinavir. Across studies, administration of KALETRA 400/100 mg twice daily yields mean steady-state lopinavir plasma concentrations 15- to 20-fold higher than those of ritonavir in HIV-1 infected patients. The plasma levels of ritonavir are less than 7% of those obtained after the ritonavir dose of 600 mg twice daily. The in vitro antiviral EC50 of lopinavir is approximately 10-fold lower than that of ritonavir. Therefore, the antiviral activity of KALETRA is due to lopinavir.

Figure 1 displays the mean steady-state plasma concentrations of lopinavir and ritonavir after KALETRA 400/100 mg twice daily with food for 3 weeks from a pharmacokinetic study in HIV-1 infected adult subjects (n = 19).

Figure 1. Mean Steady-state Plasma Concentrations with 95% Confidence Intervals (CI) for HIV-1 Infected Adult Subjects (N = 19)

Absorption
In a pharmacokinetic study in HIV-1 positive subjects (n = 19), multiple dosing with 400/100 mg KALETRA twice daily with food for 3 weeks produced a mean ± SD lopinavir peak plasma concentration (Cmax) of 9.8 ± 3.7 µg/mL, occurring approximately 4 hours after administration. The mean steady-state trough concentration prior to the morning dose was 7.1 ± 2.9 µg/mL and minimum concentration within a dosing interval was 5.5 ± 2.7 µg/mL. Lopinavir AUC over a 12 hour dosing interval averaged 92.6 ± 36.7 µg•h/mL. The absolute bioavailability of lopinavir co-formulated with ritonavir in humans has not been established. Under nonfasting conditions (500 kcal, 25% from fat), lopinavir concentrations were similar following administration of KALETRA co-formulated capsules and oral solution. When administered under fasting conditions, both the mean AUC and Cmax of lopinavir were 22% lower for the KALETRA oral solution relative to the capsule formulation.

Plasma concentrations of lopinavir and ritonavir after administration of two 200/50 mg KALETRA tablets are similar to three 133.3/33.3 mg KALETRA capsules under fed conditions with less pharmacokinetic variability.

Effects of Food on Oral Absorption
KALETRA Tablets
No clinically significant changes in Cmax and AUC were observed following administration of KALETRA tablets under fed conditions compared to fasted conditions. Relative to fasting, administration of KALETRA tablets with a moderate fat meal (500 - 682 Kcal, 23 to 25% calories from fat) increased lopinavir AUC and Cmax by 26.9% and 17.6%, respectively. Relative to fasting, administration of KALETRA tablets with a high fat meal (872 Kcal, 56% from fat) increased lopinavir AUC by 18.9% but not Cmax. Therefore, KALETRA tablets may be taken with or without food.
KALETRA Oral Solution
Relative to fasting, administration of KALETRA oral solution with a moderate fat meal (500 - 682 Kcal, 23 to 25% calories from fat) increased lopinavir AUC and Cmax by 80 and 54%, respectively. Relative to fasting, administration of KALETRA oral solution with a high fat meal (872 Kcal, 56% from fat) increased lopinavir AUC and Cmax by 130% and 56%, respectively. To enhance bioavailability and minimize pharmacokinetic variability KALETRA oral solution should be taken with food.

Distribution
At steady state, lopinavir is approximately 98-99% bound to plasma proteins. Lopinavir binds to both alpha-1-acid glycoprotein (AAG) and albumin; however, it has a higher affinity for AAG. At steady state, lopinavir protein binding remains constant over the range of observed concentrations after 400/100 mg KALETRA twice daily, and is similar between healthy volunteers and HIV-1 positive patients.

Metabolism
In vitro experiments with human hepatic microsomes indicate that lopinavir primarily undergoes oxidative metabolism. Lopinavir is extensively metabolized by the hepatic cytochrome P450 system, almost exclusively by the CYP3A isozyme. Ritonavir is a potent CYP3A inhibitor which inhibits the metabolism of lopinavir, and therefore increases plasma levels of lopinavir. A ^14C-lopinavir study in humans showed that 89% of the plasma radioactivity after a single 400/100 mg KALETRA dose was due to parent drug. At least 13 lopinavir oxidative metabolites have been identified in man. Ritonavir has been shown to induce metabolic enzymes, resulting in the induction of its own metabolism. Pre-dose lopinavir concentrations decline with time during multiple dosing, stabilizing after approximately 10 to 16 days.

Elimination
Following a 400/100 mg ^14C-lopinavir/ritonavir dose, approximately 10.4 ± 2.3% and 82.6 ± 2.5% of an administered dose of ^14C-lopinavir can be accounted for in urine and feces, respectively, after 8 days. Unchanged lopinavir accounted for approximately 2.2 and 19.8% of the administered dose in urine and feces, respectively. After multiple dosing, less than 3% of the lopinavir dose is excreted unchanged in the urine. The apparent oral clearance (CL/F) of lopinavir is 5.98 ± 5.75 L/hr (mean ± SD, n = 19).

Once Daily Dosing
The pharmacokinetics of once daily KALETRA have been evaluated in HIV-1 infected subjects naïve to antiretroviral treatment. KALETRA 800/200 mg was administered in combination with emtricitabine 200 mg and tenofovir DF 300 mg as part of a once daily regimen. Multiple dosing of 800/200 mg KALETRA once daily for 4 weeks with food (n = 24) produced a mean ± SD lopinavir peak plasma concentration (Cmax) of 11.8 ± 3.7 µg/mL, occurring approximately 6 hours after administration. The mean steady-state lopinavir trough concentration prior to the morning dose was 3.2 ± 2.1 µg/mL and minimum concentration within a dosing interval was 1.7 ± 1.6 µg/mL. Lopinavir AUC over a 24 hour dosing interval averaged 154.1 ± 61.4 µg• h/mL.

Effects on Electrocardiogram

QTcF interval was evaluated in a randomized, placebo and active (moxifloxacin 400 mg once daily) controlled crossover study in 39 healthy adults, with 10 measurements over 12 hours on Day 3. The maximum mean time-matched (95% upper confidence bound) differences in QTcF interval from placebo after baseline-correction were 5.3 (8.1) and 15.2 (18.0) mseconds (msec) for 400/100 mg twice daily and supratherapeutic 800/200 mg twice daily KALETRA, respectively. KALETRA 800/200 mg twice daily resulted in a Day 3 mean Cmax approximately 2-fold higher than the mean Cmax observed with the approved once daily and twice daily KALETRA doses at steady state.

PR interval prolongation was also noted in subjects receiving KALETRA in the same study on Day 3. The maximum mean (95% upper confidence bound) difference from placebo in the PR interval after baseline-correction were 24.9 (21.5, 28.3) and 31.9 (28.5, 35.3) msec for 400/100 mg twice daily and supratherapeutic 800/200 mg twice daily KALETRA, respectively [see Warnings and Precautions
(5.5, 5.6)].

Special Populations

Gender, Race and Age
No gender related pharmacokinetic differences have been observed in adult patients. No clinically important pharmacokinetic differences due to race have been identified. Lopinavir pharmacokinetics have not been studied in elderly patients.

Pediatric Patients
The pharmacokinetics of KALETRA oral solution 300/75 mg/m^2 twice daily and 230/57.5 mg/m^2 twice daily have been studied in a total of 53 pediatric patients in Study 940, ranging in age from 6 months to 12 years [see Clinical Studies (14.4)]. The 230/57.5 mg/m^2 twice daily regimen without nevirapine and the 300/75 mg/m^2 twice daily regimen with nevirapine provided lopinavir plasma concentrations similar to those obtained in adult patients receiving the 400/100 mg twice daily regimen (without nevirapine).

The mean steady-state lopinavir AUC, Cmax, and Cmin were 72.6 ± 31.1 µg•h/mL, 8.2 ± 2.9 and 3.4 ± 2.1 µg/mL, respectively after KALETRA oral solution 230/57.5 mg/m^2 twice daily without nevirapine (n = 12), and were 85.8 ± 36.9 µg• h/mL, 10.0 ± 3.3 and 3.6 ± 3.5 µg/mL, respectively, after 300/75 mg/m^2 twice daily with nevirapine (n = 12). The nevirapine regimen was 7 mg/kg twice daily (6 months to 8 years) or 4 mg/kg twice daily (> 8 years).

The pharmacokinetics of KALETRA oral solution at approximately 300/75 mg/m^2 twice daily have also been evaluated in infants at approximately 6 weeks of age (n = 9) and between 6 weeks and 6 months of age (n = 18) in Study 1030. The mean steady-state lopinavir AUC12, Cmax, and C12 were 43.4 ± 14.8 µg• h/mL, 5.2 ± 1.8 µg/mL and 1.9 ± 1.1 µg/mL, respectively, in infants at approximately 6 weeks of age, and 74.5 ± 37.9 µg• h/mL, 9.4 ± 4.9 and 3.1 ± 1.8 µg/mL, respectively, in infants between 6 weeks and 6 months of age after KALETRA oral solution was administered at approximately 300/75 mg/m^2 twice daily without concomitant NNRTI therapy.

The pharmacokinetics of KALETRA soft gelatin capsule and oral solution (Group 1: 400/100 mg/m^2 twice daily + 2 NRTIs; Group 2: 480/120 mg/m^2 twice daily + ≥ 1 NRTI + 1 NNRTI) have been evaluated in children and adolescents age ≥ 2 years to < 18 years of age who had failed prior therapy (n=26) in Study 1038. KALETRA doses of 400/100 and 480/120 mg/m^2 resulted in high lopinavir exposure, as almost all subjects had lopinavir AUC12 above 100 µg•h/mL. Both groups of subjects also achieved relatively high average minimum lopinavir concentrations.

KALETRA once daily has not been evaluated in pediatric patients.

Renal Impairment
Lopinavir pharmacokinetics have not been studied in patients with renal impairment; however, since the renal clearance of lopinavir is negligible, a decrease in total body clearance is not expected in patients with renal impairment.

Hepatic Impairment
Lopinavir is principally metabolized and eliminated by the liver. Multiple dosing of KALETRA 400/100 mg twice daily to HIV-1 and HCV co-infected patients with mild to moderate hepatic impairment (n = 12) resulted in a 30% increase in lopinavir AUC and 20% increase in Cmax compared to HIV-1 infected subjects with normal hepatic function (n = 12). Additionally, the plasma protein binding of lopinavir was statistically significantly lower in both mild and moderate hepatic impairment compared to controls (99.09 vs. 99.31%, respectively). Caution should be exercised when administering KALETRA to subjects with hepatic impairment. KALETRA has not been studied in patients with severe hepatic impairment [see Warnings and Precautions (5.3) and Use In Specific Populations
(8.6)].

Drug Interactions

KALETRA is an inhibitor of the P450 isoform CYP3A in vitro. Co-administration of KALETRA and drugs primarily metabolized by CYP3A may result in increased plasma concentrations of the other drug, which could increase or prolong its therapeutic and adverse effects [see Contraindications (4) and Drug Interactions (7)].

KALETRA does not inhibit CYP2D6, CYP2C9, CYP2C19, CYP2E1, CYP2B6 or CYP1A2 at clinically relevant concentrations.

KALETRA has been shown in vivo to induce its own metabolism and to increase the biotransformation of some drugs metabolized by cytochrome P450 enzymes and by glucuronidation.

KALETRA is metabolized by CYP3A. Drugs that induce CYP3A activity would be expected to increase the clearance of lopinavir, resulting in lowered plasma concentrations of lopinavir. Although not noted with concurrent ketoconazole, co-administration of KALETRA and other drugs that inhibit CYP3A may increase lopinavir plasma concentrations.

Drug interaction studies were performed with KALETRA and other drugs likely to be co-administered and some drugs commonly used as probes for pharmacokinetic interactions. The effects of co-administration of KALETRA on the AUC, Cmax and Cmin are summarized in Table 10 (effect of other drugs on lopinavir) and Table 11 (effect of KALETRA on other drugs). The effects of other drugs on ritonavir are not shown since they generally correlate with those observed with lopinavir (if lopinavir concentrations are decreased, ritonavir concentrations are decreased) unless otherwise indicated in the table footnotes. For information regarding clinical recommendations, see Table 9 in Drug Interactions (7).

Table 10. Drug Interactions: Pharmacokinetic Parameters for Lopinavir in the Presence of the Co-administered Drug for Recommended Alterations in Dose or Regimen
Co-administered Drug | Dose of Co-administered Drug (mg) | Dose of KALETRA (mg) |  | Ratio (in combination with co-administered drug/alone) of Lopinavir Pharmacokinetic Parameters (90% CI); No Effect = 1.00
 |  |  | n | Cmax | AUC | Cmin
Amprenavir | 750 twice daily, 10 d | 400/100 capsule twice daily, 21 d | 12 | 0.72 (0.65, 0.79) | 0.62 (0.56, 0.70) | 0.43 (0.34, 0.56)
Efavirenz^1,10 | 600 at bedtime, 9 d | 400/100 capsule twice daily, 9 d | 11, 7* | 0.97 (0.78, 1.22) | 0.81 (0.64, 1.03) | 0.61 (0.38, 0.97)
 | 600 at bedtime, 9 d | 500/125 tablet twice daily, 10 d | 19 | 1.12 (1.02, 1.23) | 1.06 (0.96, 1.17) | 0.90 (0.78, 1.04)
 | 600 at bedtime, 9 d | 600/150 tablet twice daily, 10 d | 23 | 1.36 (1.28, 1.44) | 1.36 (1.28, 1.44) | 1.32 (1.21, 1.44)
Fosamprenavir^2 | 700 twice daily plus ritonavir 100 twice daily, 14 d | 400/100 capsule twice daily, 14 d | 18 | 1.30 (0.85, 1.47) | 1.37 (0.80, 1.55) | 1.52 (0.72, 1.82)
Ketoconazole | 200 single dose | 400/100 capsule twice daily, 16 d | 12 | 0.89 (0.80, 0.99) | 0.87 (0.75, 1.00) | 0.75 (0.55, 1.00)
Nelfinavir | 1000 twice daily, 10 d | 400/100 capsule twice daily, 21 d | 13 | 0.79 (0.70, 0.89) | 0.73 (0.63, 0.85) | 0.62 (0.49, 0.78)
Nevirapine | 200 twice daily, steady-state (> 1 yr)3# | 400/100 capsule twice daily, steady-state | 22, 19* | 0.81 (0.62, 1.05) | 0.73 (0.53, 0.98) | 0.49 (0.28, 0.74)
 | 7 mg/kg or 4 mg/kg once daily, 2 wk; twice daily 1 wk^4 | (> 1 yr) 300/75 mg/m^2 oral solution twice daily, 3 wk | 12, 15* | 0.86 (0.64, 1.16) | 0.78 (0.56, 1.09) | 0.45 (0.25, 0.81)
Omeprazole | 40 once daily, 5 d | 400/100 tablet twice daily, 10 d | 12 | 1.08 (0.99, 1.17) | 1.07 (0.99, 1.15) | 1.03 (0.90, 1.18)
 | 40 once daily, 5 d | 800/200 tablet once daily, 10 d | 12 | 0.94 (0.88, 1.00) | 0.92 (0.86, 0.99) | 0.71 (0.57, 0.89)
Pravastatin | 20 once daily, 4 d | 400/100 capsule twice daily, 14 d | 12 | 0.98 (0.89, 1.08) | 0.95 (0.85, 1.05) | 0.88 (0.77, 1.02)
Rifabutin | 150 once daily, 10 d | 400/100 capsule twice daily, 20 d | 14 | 1.08 (0.97, 1.19) | 1.17 (1.04, 1.31) | 1.20 (0.96, 1.65)
Ranitidine | 150 single dose | 400/100 tablet twice daily, 10 d | 12 | 0.99 (0.95, 1.03) | 0.97 (0.93, 1.01) | 0.90 (0.85, 0.95)
 | 150 single dose | 800/200 tablet once daily, 10 d | 10 | 0.97 (0.95, 1.00) | 0.95 (0.91, 0.99) | 0.82 (0.74, 0.91)
Rifampin | 600 once daily, 10 d | 400/100 capsule twice daily, 20 d | 22 | 0.45 (0.40, 0.51) | 0.25 (0.21, 0.29) | 0.01 (0.01, 0.02)
 | 600 once daily, 14 d | 800/200 capsule twice daily, 9 d^5 | 10 | 1.02 (0.85, 1.23) | 0.84 (0.64, 1.10) | 0.43 (0.19, 0.96)
 | 600 once daily, 14 d | 400/400 capsule twice daily, 9 d^6 | 9 | 0.93 (0.81, 1.07) | 0.98 (0.81, 1.17) | 1.03 (0.68, 1.56)
 |  |  |  |  | Co-administration of KALETRA and rifampin is contraindicated. [see Contraindications (4)]
Ritonavir^3 | 100 twice daily, 3-4 wk# | 400/100 capsule twice daily, 3-4 wk | 8, 21* | 1.28 (0.94, 1.76) | 1.46 (1.04, 2.06) |  | 2.16 (1.29, 3.62)
Tenofovir^7 | 300 mg once daily, 14 d | 400/100 capsule twice daily, 14 d | 24 | NC† | NC† |  | NC†
Tipranavir/ritonavir^3 | 500/200 mg twice daily (28 doses)# | 400/100 capsule twice daily (27 doses) | 2169 | 0.53 (0.40, 0.69)^8 | 0.45 (0.32, 0.63)^8 |  | 0.30 (0.17, 0.51)^80.48 (0.40, 0.58)^9
All interaction studies conducted in healthy, HIV-1 negative subjects unless otherwise indicated.
1 The pharmacokinetics of ritonavir are unaffected by concurrent efavirenz.
2 Data extracted from the fosamprenavir package insert.
3 Study conducted in HIV-1 positive adult subjects.
4 Study conducted in HIV-1 positive pediatric subjects ranging in age from 6 months to 12 years.
5 Titrated to 800/200 twice daily as 533/133 twice daily x 1 d, 667/167 twice daily x 1 d, then 800/200 twice daily x 7 d, compared to 400/100 twice daily x 10 days alone.
6 Titrated to 400/400 twice daily as 400/200 twice daily x 1 d, 400/300 twice daily x 1 d, then 400/400 twice daily x 7 d, compared to 400/100 twice daily x 10 days alone.
7 Data extracted from the tenofovir package insert.
8 Intensive PK analysis.
9 Drug levels obtained at 8-16 hrs post-dose.
10 Reference for comparison is lopinavir/ritonavir 400/100 mg twice daily without efavirenz.
* Parallel group design; n for KALETRA + co-administered drug, n for KALETRA alone.
† NC = No change.
# For the nevirapine 200 mg twice daily study, ritonavir, and tipranavir/ritonavir studies, KALETRA was administered with or without food. For all other studies, KALETRA was administered with food.

Table 11. Drug Interactions: Pharmacokinetic Parameters for co-administered Drug in the Presence of KALETRA for Recommended Alterations in Dose or Regimen
Co-administered Drug | Dose of Co-administered Drug (mg) | Dose of KALETRA (mg) |  | Ratio (in combination with KALETRA/alone) of co-administered Drug Pharmacokinetic Parameters (90% CI); No Effect = 1.00
 |  |  | n | Cmax | AUC | Cmin
Amprenavir^1 | 750 twice daily, 10 d combo vs. 1200 twice daily, 14 d alone | 400/100 capsule twice daily, 21 d | 11 | 1.12 (0.91, 1.39) | 1.72 (1.41, 2.09) | 4.57 (3.51, 5.95)
Desipramine^2 | 100 single dose | 400/100 capsule twice daily, 10 d | 15 | 0.91 (0.84, 0.97) | 1.05 (0.96, 1.16) | N/A
Efavirenz | 600 at bedtime, 9 d | 400/100 capsule twice daily, 9 d | 11, 12* | 0.91 (0.72, 1.15) | 0.84 (0.62, 1.15) | 0.84 (0.58, 1.20)
Ethinyl Estradiol | 35 µg once daily, 21 d (Ortho Novum®) | 400/100 capsule twice daily, 14 d | 12 | 0.59 (0.52, 0.66) | 0.58 (0.54, 0.62) | 0.42 (0.36, 0.49)
Fosamprenavir^3 | 700 twice daily plus ritonavir 100 twice daily, 14 d | 400/100 capsule twice daily, 14 d | 18 | 0.42 (0.30, 0.58) | 0.37 (0.28, 0.49) | 0.35 (0.27, 0.46)
Indinavir^1 | 600 twice daily, 10 d combo nonfasting vs. 800 three times daily, 5 d alone fasting | 400/100 capsule twice daily, 15 d | 13 | 0.71 (0.63, 0.81) | 0.91 (0.75, 1.10) | 3.47 (2.60, 4.64)
Ketoconazole | 200 single dose | 400/100 capsule twice daily, 16 d | 12 | 1.13 (0.91, 1.40) | 3.04 (2.44, 3.79) | N/A
Methadone | 5 single dose | 400/100 capsule twice daily, 10 d | 11 | 0.55 (0.48, 0.64) | 0.47 (0.42, 0.53) | N/A
Nelfinavir^1 | 1000 twice daily, 10 d combo vs. 1250 twice daily 14 d alone | 400/100 capsule twice daily, 21 d | 13 | 0.93 (0.82, 1.05) | 1.07 (0.95, 1.19) | 1.86 (1.57, 2.22)
M8 metabolite |  |  |  | 2.36 (1.91, 2.91) | 3.46 (2.78, 4.31) | 7.49 (5.85, 9.58)
Nevirapine | 200 once daily, 14 d; twice daily, 6 d | 400/100 capsule twice daily, 20 d | 5, 6* | 1.05 (0.72, 1.52) | 1.08 (0.72, 1.64) | 1.15 (0.71, 1.86)
Norethindrone | 1 once daily, 21 d (Ortho Novum®) | 400/100 capsule twice daily, 14 d | 12 | 0.84 (0.75, 0.94) | 0.83 (0.73, 0.94) | 0.68 (0.54, 0.85)
Pravastatin | 20 once daily, 4 d | 400/100 capsule twice daily, 14 d | 12 | 1.26 (0.87, 1.83) | 1.33 (0.91, 1.94) | N/A
Rifabutin | 150 once daily, 10 d; combo vs. 300 once daily, 10 d; alone | 400/100 capsule twice daily, 10 d | 12 | 2.12 (1.89, 2.38) | 3.03 (2.79, 3.30) | 4.90 (3.18, 5.76)
25-O-desacetyl rifabutin |  |  |  | 23.6 (13.7, 25.3) | 47.5 (29.3, 51.8) | 94.9 (74.0, 122)
Rifabutin + 25-O-desacetyl rifabutin^4 |  |  |  | 3.46 (3.07, 3.91) | 5.73 (5.08, 6.46) | 9.53 (7.56, 12.01)
Rosuvastatin^5 | 20 mg once daily, 7 d | 400/100 tablet twice daily, 7 d | 15 | 4.66 (3.4, 6.4) | 2.08 (1.66, 2.6) | 1.04 (0.9, 1.2)
Tenofovir^6 | 300 mg once daily, 14 d | 400/100 capsule twice daily, 14 d | 24 | NC† | 1.32 (1.26, 1.38) | 1.51 (1.32, 1.66)
All interaction studies conducted in healthy, HIV-1 negative subjects unless otherwise indicated.
1 Ratio of parameters for amprenavir, indinavir, and nelfinavir, are not normalized for dose.
2 Desipramine is a probe substrate for assessing effects on CYP2D6-mediated metabolism.
3 Data extracted from the fosamprenavir package insert.
4 Effect on the dose-normalized sum of rifabutin parent and 25-O -desacetyl rifabutin active metabolite.
5 Data extracted from the rosuvastatin package insert and results presented at the 2007 Conference on Retroviruses and Opportunistic Infection (Hoody, et al, abstract L-107, poster #564).
6 Data extracted from the tenofovir package insert.
* Parallel group design; n for KALETRA + co-administered drug, n for co-administered drug alone.
N/A = Not available.
† NC = No change.

12.4 Microbiology

Mechanism of Action

Lopinavir, an inhibitor of the HIV-1 protease, prevents cleavage of the Gag-Pol polyprotein, resulting in the production of immature, non-infectious viral particles.

Antiviral Activity

The antiviral activity of lopinavir against laboratory HIV strains and clinical HIV-1 isolates was evaluated in acutely infected lymphoblastic cell lines and peripheral blood lymphocytes, respectively. In the absence of human serum, the mean 50% effective concentration (EC50) values of lopinavir against five different HIV-1 subtype B laboratory strains ranged from 10-27 nM (0.006-0.017 µg/mL, 1 µg/mL = 1.6 µM) and ranged from 4-11 nM (0.003-0.007 µg/mL) against several HIV-1 subtype B clinical isolates (n = 6). In the presence of 50% human serum, the mean EC50 values of lopinavir against these five HIV-1 laboratory strains ranged from 65-289 nM (0.04-0.18 µg/mL), representing a 7- to 11-fold attenuation. Combination antiviral drug activity studies with lopinavir in cell cultures demonstrated additive to antagonistic activity with nelfinavir and additive to synergistic activity with amprenavir, atazanavir, indinavir, saquinavir and tipranavir. The EC50 values of lopinavir against three different HIV-2 strains ranged from 12-180 nM (0.008-113 μg/mL).

Resistance

HIV-1 isolates with reduced susceptibility to lopinavir have been selected in cell culture. The presence of ritonavir does not appear to influence the selection of lopinavir-resistant viruses in cell culture.

The selection of resistance to KALETRA in antiretroviral treatment naïve patients has not yet been characterized. In a study of 653 antiretroviral treatment naïve patients (Study 863), plasma viral isolates from each patient on treatment with plasma HIV-1 RNA > 400 copies/mL at Week 24, 32, 40 and/or 48 were analyzed. No evidence of resistance to KALETRA was observed in 37 evaluable KALETRA-treated patients (0%). Evidence of genotypic resistance to nelfinavir, defined as the presence of the D30N and/or L90M substitution in HIV-1 protease, was observed in 25/76 (33%) of evaluable nelfinavir-treated patients. The selection of resistance to KALETRA in antiretroviral treatment naïve pediatric patients (Study 940) appears to be consistent with that seen in adult patients (Study 863).

Resistance to KALETRA has been noted to emerge in patients treated with other protease inhibitors prior to KALETRA therapy. In studies of 227 antiretroviral treatment naïve and protease inhibitor experienced patients, isolates from 4 of 23 patients with quantifiable (> 400 copies/mL) viral RNA following treatment with KALETRA for 12 to 100 weeks displayed significantly reduced susceptibility to lopinavir compared to the corresponding baseline viral isolates. Three of these patients had previously received treatment with a single protease inhibitor (indinavir, nelfinavir, or saquinavir) and one patient had received treatment with multiple protease inhibitors (indinavir, ritonavir, and saquinavir). All four of these patients had at least 4 substitutions associated with protease inhibitor resistance immediately prior to KALETRA therapy. Following viral rebound, isolates from these patients all contained additional substitutions, some of which are recognized to be associated with protease inhibitor resistance. However, there are insufficient data at this time to identify patterns of lopinavir-associated substitutions in isolates from patients on KALETRA therapy. The assessment of these patterns is under study.

Cross-resistance - Preclinical Studies

Varying degrees of cross-resistance have been observed among HIV-1 protease inhibitors. Little information is available on the cross-resistance of viruses that developed decreased susceptibility to lopinavir during KALETRA therapy.

The antiviral activity in cell culture of lopinavir against clinical isolates from patients previously treated with a single protease inhibitor was determined. Isolates that displayed > 4-fold reduced susceptibility to nelfinavir (n = 13) and saquinavir (n = 4), displayed < 4-fold reduced susceptibility to lopinavir. Isolates with > 4-fold reduced susceptibility to indinavir (n = 16) and ritonavir (n = 3) displayed a mean of 5.7- and 8.3-fold reduced susceptibility to lopinavir, respectively. Isolates from patients previously treated with two or more protease inhibitors showed greater reductions in susceptibility to lopinavir, as described in the following paragraph.

Clinical Studies - Antiviral Activity of KALETRA in Patients with Previous Protease Inhibitor Therapies

The clinical relevance of reduced susceptibility in cell culture to lopinavir has been examined by assessing the virologic response to KALETRA therapy in treatment-experienced patients, with respect to baseline viral genotype in three studies and baseline viral phenotype in one study.

Virologic response to KALETRA has been shown to be affected by the presence of three or more of the following amino acid substitutions in protease at baseline: L10F/I/R/V, K20M/N/R, L24I, L33F, M36I, I47V, G48V, I54L/T/V, V82A/C/F/S/T, and I84V. Table 12 shows the 48-week virologic response (HIV-1 RNA <400 copies/mL) according to the number of the above protease inhibitor resistance mutations at baseline in studies 888 and 765 [see Clinical Studies (14.2) and (14.3)] and study 957 (see below).

Table 12. Virologic Response (HIV-1 RNA <400 copies/mL) at Week 48 by Baseline KALETRA Susceptibility and by Number of Protease Substitutions Associated with Reduced Response to KALETRA^1
Number of protease inhibitor substitutions at baseline^1 | Study 888 (Single protease inhibitor-experienced^2, NNRTI-naïve) n=130 | Study 765 (Single protease inhibitor-experienced^3, NNRTI-naïve) n=56 | Study 957 (Multiple protease inhibitor-experienced^4, NNRTI-naïve) n=50
0-2 | 76/103 (74%) | 34/45 (76%) | 19/20 (95%)
3-5 | 13/26 (50%) | 8/11 (73%) | 18/26 (69%)
6 or more | 0/1 (0%) | n/a | 1/4 (25%)
1 Substitutions considered in the analysis included L10F/I/R/V, K20M/N/R, L24I, L33F, M36I, I47V, G48V, I54L/T/V, V82A/C/F/S/T, and I84V.
2 43% indinavir, 42% nelfinavir, 10% ritonavir, 15% saquinavir.
3 41% indinavir, 38% nelfinavir, 4% ritonavir, 16% saquinavir.
4 86% indinavir, 54% nelfinavir, 80% ritonavir, 70% saquinavir.

Virologic response to KALETRA therapy with respect to phenotypic susceptibility to lopinavir at baseline was examined in Study 957. In this study 56 NNRTI-naïve patients with HIV-1 RNA >1,000 copies/mL despite previous therapy with at least two protease inhibitors selected from indinavir, nelfinavir, ritonavir, and saquinavir were randomized to receive one of two doses of KALETRA in combination with efavirenz and nucleoside reverse transcriptase inhibitors (NRTIs). The EC50 values of lopinavir against the 56 baseline viral isolates ranged from 0.5- to 96-fold the wild-type EC50 value. Fifty-five percent (31/56) of these baseline isolates displayed >4-fold reduced susceptibility to lopinavir. These 31 isolates had a median reduction in lopinavir susceptibility of 18-fold. Response to therapy by baseline lopinavir susceptibility is shown in Table 13.

Table 13. HIV-1 RNA Response at Week 48 by Baseline Lopinavir Susceptibility^1
Lopinavir susceptibility^2 at baseline | HIV-1 RNA <400 copies/mL (%) | HIV-1 RNA <50 copies/mL (%)
< 10 fold | 25/27 (93%) | 22/27 (81%)
> 10 and < 40 fold | 11/15 (73%) | 9/15 (60%)
≥ 40 fold | 2/8 (25%) | 2/8 (25%)
1 Lopinavir susceptibility was determined by recombinant phenotypic technology performed by Virologic.
2 Fold change in susceptibility from wild type.

13 NONCLINICAL TOXICOLOGY

13.1 Carcinogenesis, Mutagenesis, Impairment of Fertility

Lopinavir/ritonavir combination was evaluated for carcinogenic potential by oral gavage administration to mice and rats for up to 104 weeks. Results showed an increase in the incidence of benign hepatocellular adenomas and an increase in the combined incidence of hepatocellular adenomas plus carcinoma in both males and females in mice and males in rats at doses that produced approximately 1.6-2.2 times (mice) and 0.5 times (rats) the human exposure (based on AUC0-24hr measurement) at the recommended dose of 400/100 mg KALETRA twice daily. Administration of lopinavir/ritonavir did not cause a statistically significant increase in the incidence of any other benign or malignant neoplasm in mice or rats.

Carcinogenicity studies in mice and rats have been carried out on ritonavir. In male mice, there was a dose dependent increase in the incidence of both adenomas and combined adenomas and carcinomas in the liver. Based on AUC measurements, the exposure at the high dose was approximately 4-fold for males that of the exposure in humans with the recommended therapeutic dose (400/100 mg KALETRA twice daily). There were no carcinogenic effects seen in females at the dosages tested. The exposure at the high dose was approximately 9-fold for the females that of the exposure in humans. There were no carcinogenic effects in rats. In this study, the exposure at the high dose was approximately 0.7-fold that of the exposure in humans with the 400/100 mg KALETRA twice daily regimen. Based on the exposures achieved in the animal studies, the significance of the observed effects is not known. However, neither lopinavir nor ritonavir was found to be mutagenic or clastogenic in a battery of in vitro and in vivo assays including the Ames bacterial reverse mutation assay using S. typhimurium and E. coli, the mouse lymphoma assay, the mouse micronucleus test and chromosomal aberration assays in human lymphocytes.

Lopinavir in combination with ritonavir at a 2:1 ratio produced no effects on fertility in male and female rats at levels of 10/5, 30/15 or 100/50 mg/kg/day. Based on AUC measurements, the exposures in rats at the high doses were approximately 0.7-fold for lopinavir and 1.8-fold for ritonavir of the exposures in humans at the recommended therapeutic dose (400/100 mg twice daily).

14 CLINICAL STUDIES

14.1 Patients Without Prior Antiretroviral Therapy

Study 863: KALETRA Capsules twice daily + stavudine + lamivudine compared to nelfinavir three-times daily + stavudine + lamivudine

Study 863 was a randomized, double-blind, multicenter trial comparing treatment with KALETRA capsules (400/100 mg twice daily) plus stavudine and lamivudine versus nelfinavir (750 mg three-times daily) plus stavudine and lamivudine in 653 antiretroviral treatment naïve patients. Patients had a mean age of 38 years (range: 19 to 84), 57% were Caucasian, and 80% were male. Mean baseline CD4^+ cell count was 259 cells/mm^3 (range: 2 to 949 cells/mm^3) and mean baseline plasma HIV-1 RNA was 4.9 log10 copies/mL (range: 2.6 to 6.8 log10 copies/mL).

Treatment response and outcomes of randomized treatment are presented in Table 14.

Table 14. Outcomes of Randomized Treatment Through Week 48 (Study 863)
Outcome | KALETRA+d4T+3TC (N = 326) | Nelfinavir+d4T+3TC (N = 327)
Responder^1 | 75% | 62%
Virologic failure^2 Rebound Never suppressed through Week 48 | 9% 7% 2% | 25% 15% 9%
Death | 2% | 1%
Discontinued due to adverse events | 4% | 4%
Discontinued for other reasons^3 | 10% | 8%
1 Patients achieved and maintained confirmed HIV-1 RNA < 400 copies/mL through Week 48.
2 Includes confirmed viral rebound and failure to achieve confirmed < 400 copies/mL through Week 48.
3 Includes lost to follow-up, patient's withdrawal, non-compliance, protocol violation and other reasons. Overall discontinuation through Week 48, including patients who discontinued subsequent to virologic failure, was 17% in the KALETRA arm and 24% in the nelfinavir arm.

Through 48 weeks of therapy, there was a statistically significantly higher proportion of patients in the KALETRA arm compared to the nelfinavir arm with HIV-1 RNA < 400 copies/mL (75% vs. 62%, respectively) and HIV-1 RNA < 50 copies/mL (67% vs. 52%, respectively). Treatment response by baseline HIV-1 RNA level subgroups is presented in Table 15.

Table 15. Proportion of Responders Through Week 48 by Baseline Viral Load (Study 863)
Baseline Viral Load (HIV-1 RNA copies/mL) | KALETRA +d4T+3TC |  |  | Nelfinavir +d4T+3TC
 | <400 copies/mL ^1 | <50 copies/mL ^2 | n | <400 copies/mL ^1 | <50 copies/mL ^2 | n
< 30,000 | 74% | 71% | 82 | 79% | 72% | 87
≥ 30,000 to < 100,000 | 81% | 73% | 79 | 67% | 54% | 79
≥ 100,000 to < 250,000 | 75% | 64% | 83 | 60% | 47% | 72
≥ 250,000 | 72% | 60% | 82 | 44% | 33% | 89
1 Patients achieved and maintained confirmed HIV-1 RNA < 400 copies/mL through Week 48.
2 Patients achieved HIV-1 RNA < 50 copies/mL at Week 48.

Through 48 weeks of therapy, the mean increase from baseline in CD4^+ cell count was 207 cells/mm^3 for the KALETRA arm and 195 cells/mm^3 for the nelfinavir arm.

Study 730: KALETRA Tablets once daily + tenofovir DF + emtricitabine compared to KALETRA Tablets twice daily + tenofovir DF + emtricitabine.

Study 730 was a randomized, open-label, multicenter trial comparing treatment with KALETRA 800/200 mg once daily plus tenofovir DF and emtricitabine versus KALETRA 400/100 mg twice daily plus tenofovir DF and emtricitabine in 664 antiretroviral treatment-naïve patients. Patients were randomized in a 1:1 ratio to receive either KALETRA 800/200 mg once daily (n = 333) or KALETRA 400/100 mg twice daily (n = 331). Further stratification within each group was 1:1 (tablet vs. capsule). Patients administered the capsule were switched to the tablet formulation at Week 8 and maintained on their randomized dosing schedule. Patients were administered emtricitabine 200 mg once daily and tenofovir DF 300 mg once daily. Mean age of patients enrolled was 39 years (range: 19 to 71); 75% were Caucasian, and 78% were male. Mean baseline CD4+ cell count was 216 cells/mm^3 (range: 20 to 775 cells/mm^3) and mean baseline plasma HIV-1 RNA was 5.0 log10 copies/mL (range: 1.7 to 7.0 log10 copies/mL).

Treatment response and outcomes of randomized treatment through Week 48 are presented in Table 16.

Table 16. Outcomes of Randomized Treatment Through Week 48 (Study 730)
Outcome | KALETRA Once Daily + TDF + FTC (n = 333) | KALETRA Twice Daily + TDF + FTC (n = 331)
Responder^1 | 78% | 77%
Virologic failure^2 Rebounded Never suppressed through Week 48 | 10% 5% 5% | 8% 5% 3%
Death | 1% | <1%
Discontinued due to adverse events | 4% | 3%
Discontinued for other reasons^3 | 8% | 11%
1 Patients achieved and maintained confirmed HIV-1 RNA < 50 copies/mL through Week 48.
2 Includes confirmed viral rebound and failure to achieve confirmed < 50 copies/mL through Week 48.
3 Includes lost to follow-up, patient's withdrawal, non-compliance, protocol violation and other reasons.

Through 48 weeks of therapy, 78% in the KALETRA once daily arm and 77% in the KALETRA twice daily arm achieved and maintained HIV-1 RNA < 50 copies/mL (95% confidence interval for the difference, -5.9% to 6.8%). Mean CD4+ cell count increases at Week 48 were 186 cells/mm^3 for the KALETRA once daily arm and 198 cells/mm^3 for the KALETRA twice daily arm.

14.2 Patients With Prior Antiretroviral Therapy

Study 888: KALETRA Capsules twice daily + nevirapine + NRTIs compared to investigator-selected protease inhibitor(s) + nevirapine + NRTIs

Study 888 was a randomized, open-label, multicenter trial comparing treatment with KALETRA capsules (400/100 mg twice daily) plus nevirapine and nucleoside reverse transcriptase inhibitors versus investigator-selected protease inhibitor(s) plus nevirapine and nucleoside reverse transcriptase inhibitors in 288 single protease inhibitor-experienced, non-nucleoside reverse transcriptase inhibitor (NNRTI)-naïve patients. Patients had a mean age of 40 years (range: 18 to 74), 68% were Caucasian, and 86% were male. Mean baseline CD4^+cell count was 322 cells/mm^3 (range: 10 to 1059 cells/mm^3) and mean baseline plasma HIV-1 RNA was 4.1 log10 copies/mL (range: 2.6 to 6.0 log10 copies/mL).

Treatment response and outcomes of randomized treatment through Week 48 are presented in Table 17.

Table 17. Outcomes of Randomized Treatment Through Week 48 (Study 888)
Outcome | KALETRA + nevirapine + NRTIs (n = 148) | Investigator-Selected Protease Inhibitor(s) + nevirapine + NRTIs (n = 140)
Responder^1 | 57% | 33%
Virologic failure^2 | 24% | 41%
Rebound Never suppressed through Week 48 | 11% 13% | 19% 23%
Death | 1% | 2%
Discontinued due to adverse events | 5% | 11%
Discontinued for other reasons^3 | 14% | 13%
1 Patients achieved and maintained confirmed HIV-1 RNA < 400 copies/mL through Week 48.
2 Includes confirmed viral rebound and failure to achieve confirmed < 400 copies/mL through Week 48.
3 Includes lost to follow-up, patient's withdrawal, non-compliance, protocol violation and other reasons.

Through 48 weeks of therapy, there was a statistically significantly higher proportion of patients in the KALETRA arm compared to the investigator-selected protease inhibitor(s) arm with HIV-1 RNA < 400 copies/mL (57% vs. 33%, respectively).

Through 48 weeks of therapy, the mean increase from baseline in CD4^+ cell count was 111 cells/mm^3 for the KALETRA arm and 112 cells/mm^3 for the investigator-selected protease inhibitor(s) arm.

14.3 Other Studies Supporting Approval

Study 720: KALETRA twice daily + stavudine + lamivudine
Study 765: KALETRA twice daily + nevirapine + NRTIs

Study 720 (patients without prior antiretroviral therapy) and study 765 (patients with prior protease inhibitor therapy) were randomized, blinded, multi-center trials evaluating treatment with KALETRA at up to three dose levels (200/100 mg twice daily [720 only], 400/100 mg twice daily, and 400/200 mg twice daily). In Study 720, all patients switched to 400/100 mg twice daily between Weeks 48-72. Patients in study 720 had a mean age of 35 years, 70% were Caucasian, and 96% were male, while patients in study 765 had a mean age of 40 years, 73% were Caucasian, and 90% were male. Mean (range) baseline CD4^+ cell counts for patients in study 720 and study 765 were 338 (3-918) and 372 (72-807) cells/mm^3, respectively. Mean (range) baseline plasma HIV-1 RNA levels for patients in study 720 and study 765 were 4.9 (3.3 to 6.3) and 4.0 (2.9 to 5.8) log10 copies/mL, respectively.

Through 360 weeks of treatment in study 720, the proportion of patients with HIV-1 RNA < 400 (< 50) copies/mL was 61% (59%) [n = 100]. Among patients completing 360 weeks of treatment with CD4^+ cell count measurements [n=60], the mean (median) increase in CD4^+cell count was 501 (457) cells/mm^3. Thirty-nine patients (39%) discontinued the study, including 13 (13%) discontinuations due to adverse reactions and 1 (1%) death.

Through 144 weeks of treatment in study 765, the proportion of patients with HIV-1 RNA < 400 (< 50) copies/mL was 54% (50%) [n = 70], and the corresponding mean increase in CD4^+cell count was 212 cells/mm^3. Twenty-seven patients (39%) discontinued the study, including 5 (7%) discontinuations secondary to adverse reactions and 2 (3%) deaths.

14.4 Pediatric Studies

Study 1030 was an open-label, multicenter, dose-finding trial evaluating the pharmacokinetic profile, tolerability, safety and efficacy of KALETRA oral solution containing lopinavir 80 mg/mL and ritonavir 20 mg/mL at a dose of 300/75 mg/m^2 twice daily plus 2 NRTIs in HIV-1 infected infants ≥14 days and <6 months of age.

Ten infants, ≥14 days and <6 wks of age, were enrolled at a median (range) age of 5.7 (3.6-6.0) weeks and all completed 24 weeks. At entry, median (range) HIV-1 RNA was 6.0 (4.7-7.2) log10 copies/mL. Seven of 10 infants had HIV-1 RNA <400 copies/mL at Week 24. At entry, median (range) CD4^+ percentage was 41 (16-59) with a median decrease of 1% (95% CI: -10, 18) from baseline to week 24 in 6 infants with available data.

Twenty-one infants, between 6 weeks and 6 months of age, were enrolled at a median (range) age of 14.7 (6.9-25.7) weeks and 19 of 21 infants completed 24 weeks. At entry, median (range) HIV RNA level was 5.8 (3.7-6.9) log10 copies/mL. Ten of 21 infants had HIV RNA <400 copies/mL at Week 24. At entry, the median (range) CD4^+ percentage was 32 (11-54) with a median increase of 4% (95% CI: -1, 9) from baseline to week 24 in 19 infants with available data.

See Clinical Pharmacology (12.3) for pharmacokinetic results.

Study 940 was an open-label, multicenter trial evaluating the pharmacokinetic profile, tolerability, safety and efficacy of KALETRA oral solution containing lopinavir 80 mg/mL and ritonavir 20 mg/mL in 100 antiretroviral naïve (44%) and experienced (56%) pediatric patients. All patients were non-nucleoside reverse transcriptase inhibitor naïve. Patients were randomized to either 230 mg lopinavir/57.5 mg ritonavir per m^2 or 300 mg lopinavir/75 mg ritonavir per m^2. Naïve patients also received lamivudine and stavudine. Experienced patients received nevirapine plus up to two nucleoside reverse transcriptase inhibitors.

Safety, efficacy and pharmacokinetic profiles of the two dose regimens were assessed after three weeks of therapy in each patient. After analysis of these data, all patients were continued on the 300 mg lopinavir/75 mg ritonavir per m^2 dose. Patients had a mean age of 5 years (range 6 months to 12 years) with 14% less than 2 years. Mean baseline CD4^+ cell count was 838 cells/mm^3 and mean baseline plasma HIV-1 RNA was 4.7 log10 copies/mL.

Through 48 weeks of therapy, the proportion of patients who achieved and sustained an HIV-1 RNA < 400 copies/mL was 80% for antiretroviral naïve patients and 71% for antiretroviral experienced patients. The mean increase from baseline in CD4^+cell count was 404 cells/mm^3 for antiretroviral naïve and 284 cells/mm^3 for antiretroviral experienced patients treated through 48 weeks. At 48 weeks, two patients (2%) had prematurely discontinued the study. One antiretroviral naïve patient prematurely discontinued secondary to an adverse reaction, while one antiretroviral experienced patient prematurely discontinued secondary to an HIV-1 related event.

Dose selection in pediatric patients was based on the following:

- Among patients 14 days to 6 months of age receiving 300/75 mg/m^2 twice daily without nevirapine, plasma concentrations were lower than those observed in adults or in older children. This dose resulted in HIV-1 RNA < 400 copies/mL in 55% of patients (70% in those initiating treatment at <6 weeks of age).
- Among patients 6 months to 12 years of age, the 230/57.5 mg/m^2 oral solution twice daily regimen without nevirapine and the 300/75 mg/m^2 oral solution twice daily regimen with nevirapine provided lopinavir plasma concentrations similar to those obtained in adult patients receiving the 400/100 mg twice daily regimen (without nevirapine). These doses resulted in treatment benefit (proportion of patients with HIV-1 RNA < 400 copies/mL) similar to that seen in the adult clinical trials.
- Among patients 12 to 18 years of age receiving 400/100 mg/m^2 or 480/120 mg/m^2 (with efavirenz) twice daily, plasma concentrations were 60-100% higher than among 6 to 12 year old patients receiving 230/57.5 mg/m^2. Mean apparent clearance was similar to that observed in adult patients receiving standard dose and in patients 6 to 12 years of age. Although changes in HIV-1 RNA in patients with prior treatment failure were less than anticipated, the pharmacokinetic data supports use of similar dosing as in patients 6 to 12 years of age, not to exceed the recommended adult dose.
- For all age groups, the body surface area dosing was converted to body weight dosing using the actual patient dose.

16 HOW SUPPLIED/STORAGE AND HANDLING

KALETRA® (lopinavir/ritonavir) Film-Coated tablets and Oral Solution are available in the following strengths and package sizes:

16.1 KALETRA Tablets, 200 mg lopinavir/50 mg ritonavir

Yellow film-coated ovaloid tablets debossed with the corporate Abbott “A” logo and the Abbo-Code KA.

Recommended Storage:

Store KALETRA film-coated tablets at 20°-25°C (68°-77°F); excursions permitted to 15°-30°C (59° to 86°F)[see USP controlled room temperature]. Dispense in original container or USP equivalent tight container (250 mL or less). For patient use: exposure of this product to high humidity outside the original container or USP equivalent tight container (250 mL or less) for longer than 2 weeks is not recommended.

16.2 KALETRA Tablets, 100 mg lopinavir/25 mg ritonavir

Pale yellow film-coated ovaloid tablets debossed with the corporate Abbott “A” logo and the Abbo-Code KC.

Recommended Storage:

Store KALETRA film-coated tablets at 20°-25°C (68°-77°F); excursions permitted to 15°-30°C (59° to 86°F)[see USP controlled room temperature]. Dispense in original container or USP equivalent tight container (100 mL or less). For patient use: exposure of this product to high humidity outside the original container or USP equivalent tight container (100 mL or less) for longer than 2 weeks is not recommended.

They are supplied by State of Florida DOH Central Pharmacy as follows:

NDC | Strength | Quantity/Form | Color | Source Prod. Code
53808-0276-1 | 200 mg / 50 mg | 30 Tablets in a Blister Pack | YELLOW | 0074-6799

17 PATIENT COUNSELING INFORMATION

See Medication Guide (17)

17.1 Information For Patients

Patients or parents of patients should be informed that:

General Information
They should pay special attention to accurate administration of their dose to minimize the risk of accidental overdose or underdose of KALETRA.
They should inform their healthcare provider if their children’s weight changes in order to make sure that the child’s KALETRA dose is the correct one.
They should take the prescribed dose of KALETRA as directed and to set up a daily routine in order to do so.
KALETRA tablets may be taken with or without food. KALETRA oral solution should be taken with food to enhance absorption.
Sustained decreases in plasma HIV-1 RNA have been associated with a reduced risk of progression to AIDS and death. Patients should remain under the care of a physician while using KALETRA. Patients should be advised to take KALETRA and other concomitant antiretroviral therapy every day as prescribed. KALETRA must always be used in combination with other antiretroviral drugs. Patients should not alter the dose or discontinue therapy without consulting with their doctor. If a dose of KALETRA is missed patients should take the dose as soon as possible and then return to their normal schedule. However, if a dose is skipped the patient should not double the next dose.
KALETRA is not a cure for HIV-1 infection and that they may continue to develop opportunistic infections and other complications associated with HIV-1 disease. The long-term effects of KALETRA are unknown at this time. Patients should be told that there are currently no data demonstrating that therapy with KALETRA can reduce the risk of transmitting HIV-1 to others through sexual contact, sharing needles, or being exposed to their blood. For their health and the health of others, it is important that they always practice safer sex by using a latex or polyurethane condom or other barrier method to lower the chance of sexual contact with any body fluids such as semen, vaginal secretions, or blood. They should also be advised to never re-use or share needles.

Drug Interactions
KALETRA may interact with some drugs; therefore, patients should be advised to report to their doctor the use of any other prescription, non-prescription medication or herbal products, particularly St. John's Wort.
KALETRA tablets can be taken at the same time as didanosine without food. Patients taking didanosine should take didanosine one hour before or two hours after KALETRA oral solution.
If they are receiving sildenafil, tadalafil, or vardenafil, there may be at an increased risk of associated adverse reactions including hypotension, visual changes, and sustained erection, and should promptly report any symptoms to their doctor.
If they are receiving estrogen-based hormonal contraceptives, additional or alternate contraceptive measures should be used during therapy with KALETRA.

Potential Adverse Effects
Skin rashes ranging in severity from mild to Stevens Johnson syndrome and Erythema multiforme have been reported in patients receiving KALETRA or its components lopinavir and/or ritonavir. Patients should be advised to contact their healthcare provider if they develop a rash while taking KALETRA. The healthcare provider will determine if treatment should be continued or an alternative antiretroviral regimen used.
Pre-existing liver disease including Hepatitis B or C can worsen with use of KALETRA. This can be seen as worsening of transaminase elevations or hepatic decompensation. Patients should be advised that their liver function tests will need to be monitored closely especially during the first several months of KALETRA treatment and that they should notify their healthcare provider if they develop the signs and symptoms of worsening liver disease including loss of appetite, abdominal pain, jaundice, and itchy skin.
New onset of diabetes or exacerbation of pre-existing diabetes mellitus, and hyperglycemia have been reported during KALETRA use. Patients should be advised to notify their healthcare provider if they develop the signs and symptoms of diabetes mellitus including frequent urination, excessive thirst, extreme hunger or unusual weight loss and/or an increased blood sugar while on KALETRA as they may require a change in their diabetes treatment or new treatment.
KALETRA might produce changes in the electrocardiogram (e.g., PR and/or QT prolongation). Patients should consult their physician if they experience symptoms such as dizziness, lightheadedness, abnormal heart rhythm or loss of consciousness.
They should seek medical assistance immediately if they develop a sustained penile erection lasting more than 4 hours while taking KALETRA and a PDE 5 Inhibitor such as Viagra, Cialis or Levitra.
Redistribution or accumulation of body fat may occur in patients receiving antiretroviral therapy and that the cause and long term health effects of these conditions are not known at this time.
Patients should be informed that there may be a greater chance of developing diarrhea with the once daily regimen as compared with the twice daily regimen.

Medication Guide

KALETRA® (kuh-LEE-tra)

(lopinavir/ritonavir)

Tablets

KALETRA® (kuh-LEE-tra)

(lopinavir/ritonavir)

Oral Solution

Read the Medication Guide that comes with KALETRA before you start taking it and each time you get a refill. There may be new information. This information does not take the place of talking with your doctor about your medical condition or treatment. You and your doctor should talk about your treatment with KALETRA before you start taking it and at regular check-ups. You should stay under your doctor’s care when taking KALETRA.

What is the most important information I should know about KALETRA?

KALETRA may cause serious side effects, including:

- Interactions with other medicines. It is important to know the medicines that should not be taken with KALETRA. Read the section "What should I tell my doctor before taking KALETRA?”
- Changes in your heart rhythm and the electrical activity of your heart. These changes may be seen on an EKG (electrocardiogram) and can lead to serious heart problems. Your risk for these problems may be higher if you:
  - already have a history of abnormal heart rhythm or other types of heart disease
  - take other medicines that can affect your heart rhythm while you take KALETRA.

Tell your doctor right away if you have any of these symptoms while taking KALETRA:

- dizziness
- lightheadedness
- fainting
- sensation of abnormal heartbeats

See the section below “What are the possible side effects of KALETRA?” for more information about serious side effects.

What is KALETRA?

KALETRA is a prescription anti-HIV medicine that contains two medicines: lopinavir and ritonavir. KALETRA is called a protease inhibitor that is used with other anti-HIV-1 medicines to treat people with human immunodeficiency virus (HIV-1) infection. HIV-1 is the virus that causes AIDS (Acquired Immune Deficiency Syndrome).

It is not known if KALETRA is safe and effective in children under 14 days old.

Who should not take KALETRA?

- Do not take KALETRA if you are taking certain medicines. For more information about medicines you should not take with KALETRA, please see “Can I take other medicines with KALETRA?” and consult with your doctor about all other medicines you take.
- Do not take KALETRA if you have an allergy to KALETRA or any of its ingredients, including ritonavir and lopinavir.

What should I tell my doctor before taking KALETRA?

Kaletra may not be right for you. Tell your doctor about all your medical conditions, including if you:

- have any heart problems, including if you have a condition called Congenital Long QT Syndrome.
- have liver problems, including Hepatitis B or Hepatitis C.
- have diabetes.
- have hemophilia. People who take KALETRA may have increased bleeding.
- have low potassium in your blood.
- are pregnant or plan to become pregnant. It is not known if KALETRA will harm your unborn baby. Birth control pills or patches may not work as well while you take KALETRA. To prevent pregnancy while taking KALETRA, women who take birth control pills or use estrogen patch for birth control should either use a different type of birth control or an extra form of birth control. Talk to your doctor about how to prevent pregnancy while taking KALETRA.
- take KALETRA during pregnancy, talk with your doctor about how you can take part in an antiretroviral pregnancy registry. The purpose of the pregnancy registry is to follow the health of you and your baby.
- are breast-feeding. Do not breast-feed if you are taking KALETRA. You should not breast-feed if you have HIV-1. If you are a woman who has or will have a baby while taking KALETRA, talk with your doctor about the best way to feed your baby. If your baby does not already have HIV-1, there is a chance that HIV-1 can be passed to your baby through your breast milk.

Tell your doctor about all the medicines you take, including prescription and non-prescription medicines, vitamins, and herbal supplements. Many medicines interact with KALETRA. Do not start taking a new medicine without telling your doctor or pharmacist. Your doctor can tell you if it is safe to take KALETRA with other medicines. Your doctor may need to change the dose of other medicines while you take KALETRA.

Medicines you should not take with KALETRA.

Serious problems or death can happen if you take these medicines with KALETRA:

- ergot containing medicines, including:
  - ergotamine tartrate (Cafergot®, Migergot, Ergomar, Ergostat, Medihaler Ergotamine, Wigraine, Wigrettes)
  - dihydroergotamine mesylate (D.H.E. 45®, Embolex, Migranal®)
  - ergonovine, ergonovine and methylergonovine (Ergotrate, Methergine), ergotamine and methylergonovine
  - Ergotrate Maleate, methylergonovine maleate (Methergine)
- triazolam (Halcion®), midazolam hydrochloride oral syrup
- pimozide (Orap®)
- the cholesterol lowering medicines lovastatin (Mevacor®) or simvastatin (Zocor®)

Medicines that you should not take with KALETRA since they may make KALETRA not work as well:

- the herbal supplement St Johns Wort (hypericum perforatum)
- rifampin (Rimactane®, Rifadin®, Rifater®, or Rifamate®)

Medicines that may need changes:

- birth control pills that contain estrogen ("the pill") or the birth control (contraceptive) patches
- certain cholesterol lowering medicines, such as atorvastatin (Lipitor®) or rosuvastatin (Crestor®)
- certain other antiretroviral medicines, such as efavirenz (Atripla® and Sustiva®), nevirapine (Viramune®), amprenavir (Agenerase®), fosamprenavir calcium (Lexiva®) and nelfinavir (Viracept®)
- anti-seizure medicines, such as phenytoin (Dilantin®) carbamazepine, (Tegretol®), phenobarbital
- sildenafil (Viagra®, Revatio®), tadalafil (Cialis®), or vardenafil (Levitra®)
- medicines for tuberculosis (TB), such as rifabutin (Mycobutin®)
- inhaled steroid medicines, such as fluticasone propionate (Flonase®)

If you are not sure if you are taking a medicine above, ask your doctor.

How should I take KALETRA?

- Take KALETRA every day exactly as prescribed by your doctor.
- It is very important to set up a dosing schedule and follow it every day.
- Do not change your treatment or stop treatment without first talking with your doctor.
- Swallow KALETRA tablets whole. Do not chew, break, or crush KALETRA tablets.
- KALETRA tablets can be taken with or without food.
- If you are taking both Videx® (didanosine) and KALETRA:
  - didanosine can be taken at the same time as KALETRA tablets, without food.
  - take didanosine either one hour before or two hours after taking KALETRA oral solution.
- Do not miss a dose of KALETRA. This could make the virus harder to treat. If you forget to take KALETRA, take the missed dose right away. If it is almost time for your next dose, do not take the missed dose. Instead, follow your regular dosing schedule by taking your next dose at its regular time. Do not take more than one dose of KALETRA at one time.
- If you take more than the prescribed dose of KALETRA, call your local poison control center or emergency room right away.
- Take KALETRA oral solution with food to help it work better.
- If KALETRA is being used for your child, tell your doctor if your child’s weight changes.
- KALETRA should not be given one time each day in children. When giving KALETRA to your child, give KALETRA exactly as prescribed.
- KALETRA oral solution contains a large amount of alcohol.
  - If a young child drinks more than the recommended dose, it could make them sick from too much alcohol. Contact your local poison control center or emergency room right away.
  - Talk with your doctor if you take or plan to take metronidazole or disulfiram. You can have severe nausea and vomiting if you take these medicines with KALETRA.
- When your KALETRA supply starts to run low, get more from your doctor or pharmacy. It is important not to run out of KALETRA. The amount of HIV-1 virus in your blood may increase if the medicine is stopped for even a short time. The virus may become resistant to KALETRA and become harder to treat.
- KALETRA can be taken with acid reducing agents used for heartburn or reflux (such as Prilosec® (omeprazole) and Zantac® (ranitidine) with no dose adjustment.

Avoid doing things that can spread HIV infection. KALETRA does not stop you from passing HIV infection to others. Do not share needles, other injection equipment or personal items that can have blood or body fluids on them, like toothbrushes and razor blades. Always practice safer sex by using a latex or polyurethane condom to lower the chance of sexual contact with semen, vaginal secretions, or blood.

What are the possible side effects of KALETRA?

KALETRA can cause serious side effects.

- See “What is the most important information I should know about KALETRA?”
- Liver problems. Liver problems, including death, can happen in people who take KALETRA. Blood tests in people who take KALETRA may show possible liver problems. People with liver disease such as Hepatitis B and Hepatitis C who take KALETRA may have worsening liver disease. Tell your healthcare provider right away if you have any of these signs and symptoms of liver problems:
  - loss of appetite
  - yellow skin and whites of eyes (jaundice)
  - dark-colored urine
  - pale colored stools, itchy skin
  - stomach area (abdominal) pain.
- Inflammation of the pancreas (pancreatitis). Some people who take KALETRA get inflammation of the pancreas which may be serious and cause death. You have a higher chance of getting pancreatitis if you have had it before. Tell your doctor if you have nausea, vomiting, or abdominal pain while taking KALETRA. These may be signs of pancreatitis.
- Increases in certain fat (triglycerides and cholesterol) levels in your blood. Large increases of triglycerides and cholesterol can be seen in blood test results of some people who take KALETRA. The long-term chance of getting complications such as heart attacks or stroke due to increases in triglycerides and cholesterol caused by protease inhibitors is not known at this time.
- Diabetes and high blood sugar (hyperglycemia). Some people who take protease inhibitors including KALETRA get new or more serious diabetes, or high blood sugar. Tell your doctor if you notice an increase in thirst or urinate often while taking KALETRA.
- Changes in body fat. Changes in body fat in some people who take antiretroviral therapy. These changes may include increased amount of fat in the upper back and neck ("buffalo hump"), breast, and around the trunk. Loss of fat from the legs, arms and face may also happen. The cause and long-term health effects of these conditions are not known at this time.
- Increased bleeding for hemophiliacs. Some people with hemophilia have increased bleeding with protease inhibitors including KALETRA.
- Increased risk of certain problems when you take medicines such as sildenafil (Viagra®, Revatio®), tadalafil (Cialis®), or vardenafil (Levitra ®) with KALETRA:
  - low blood pressure. If you get dizzy or faint, you need to lie down. Tell your doctor if you feel dizzy, or have fainting spells.
  - vision changes. Tell your doctor right away if you have vision changes.
  - penis erection lasting more than 4 hours. If you are a male and have an erection that lasts longer than 4 hours, get medical help right away to avoid permanent damage to your penis. Your doctor can explain these symptoms to you.

Common side effects of KALETRA include:

- diarrhea
- nausea
- stomach area (abdominal) pain
- feeling weak
- vomiting
- headache
- upset stomach

These are not all of the possible side effects of KALETRA. For more information, ask your doctor or pharmacist. Tell your doctor about any side effect that bothers you or that does not go away.

Call your doctor for medical advice about side effects. You may report side effects to FDA at 1-800-FDA-1088.

How should I store KALETRA?

KALETRA tablets:

- Store KALETRA tablets at room temperature, between 59°F to 86°F (15°C to 30°C).
- Do not keep KALETRA tablets out of the container it comes in for longer than 2 weeks, especially in areas where there is a lot of humidity. Keep the container closed tightly.

KALETRA oral solution:

- Store KALETRA oral solution in a refrigerator, between 36°F to 46°F (2°C to 8°C). KALETRA oral solution that is kept refrigerated may be used until the expiration date printed on the label.
- KALETRA oral solution that is stored at room temperature (less than 77°F or 25°C) should be used within 2 months.
- Keep KALETRA away from high heat.

Throw away any medicine that is out of date or that you no longer need.

Keep KALETRA and all medicines out of the reach of children.

General information about KALETRA

KALETRA does not cure HIV-1 or AIDS. The long-term effects of KALETRA are not known at this time. People taking KALETRA may still get opportunistic infections or other conditions that happen with HIV-1 infection. Some of these conditions are pneumonia, herpes virus infections, and Mycobacterium avium complex (MAC) infections.

Medicines are sometimes prescribed for purposes other than those listed in a Medication Guide. Do not use KALETRA for a condition for which it was not prescribed. Do not give KALETRA to other people, even if they have the same condition you have. It may harm them.

This Medication Guide summarizes the most important information about KALETRA. If you would like more information, talk with your doctor. You can ask your pharmacist or doctor for information about KALETRA that is written for health professionals. For more information about KALETRA call 1-800-633-9110 or go to www.KALETRA.com.

What are the ingredients in KALETRA?

Active ingredient: lopinavir and ritonavir

Inactive ingredients:

KALETRA 200 mg lopinavir and 50 mg ritonavir tablets: copovidone, sorbitan monolaurate, colloidal silicon dioxide, and sodium stearyl fumarate. The film coating contains: hypromellose, titanium dioxide, polyethylene glycol 400, hydroxypropyl cellulose, talc, colloidal silicon dioxide, polyethylene glycol 3350, yellow ferric oxide 172, and polysorbate 80.

KALETRA 100 mg lopinavir and 25 mg ritonavir tablets: copovidone, sorbitan monolaurate, colloidal silicon dioxide, and sodium stearyl fumarate. The film coating contains: polyvinyl alcohol, titanium dioxide, talc, polytheylene glycol 3350, and yellow ferric oxide E172.

KALETRA oral solution: acesulfame potassium, alcohol, artificial cotton candy flavor, citric acid, glycerin, high fructose corn syrup, Magnasweet-110 flavor, menthol, natural and artificial vanilla flavor, peppermint oil, polyoxyl 40 hydrogenated castor oil, povidone, propylene glycol, saccharin sodium, sodium chloride, sodium citrate, and water.

KALETRA oral solution contains 42.4% alcohol (v/v). “See How should I take KALETRA?”.

KALETRA Tablets, 200 mg lopinavir/50 mg ritonavir
Manufactured by Abbott Pharmaceuticals PR Ltd., Barceloneta, PR 00617
for Abbott Laboratories, North Chicago, IL 60064, U.S.A.

* The brands listed are trademarks of their respective owners and are not trademarks of Abbott Laboratories. The makers of these brands are not affiliated with and do not endorse Abbott Laboratories or its products.

This Medication Guide has been approved by the U.S. Food and Drug Administration.

This Product was Repackaged By:

State of Florida DOH Central Pharmacy
104-2 Hamilton Park Drive
Tallahassee, FL 32304
United States

PACKAGE LABEL

NDC 53808-0276-1

Kaletra® (Lopinavir/Ritonavir) Tablets 200 mg/50 mg 30 tablets

ALERT: Find out about medicines that should NOT be taken with Kaletra®

Attention Pharmacist: Do not cover ALERT box with pharmacy label. Dispense the accompanying Medication Guide to each patient.

Rx only Abbott